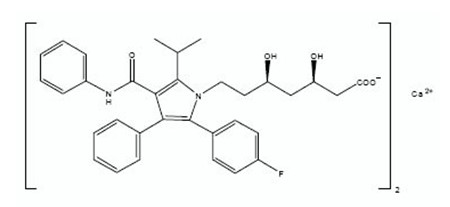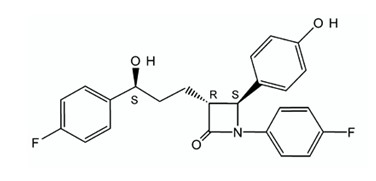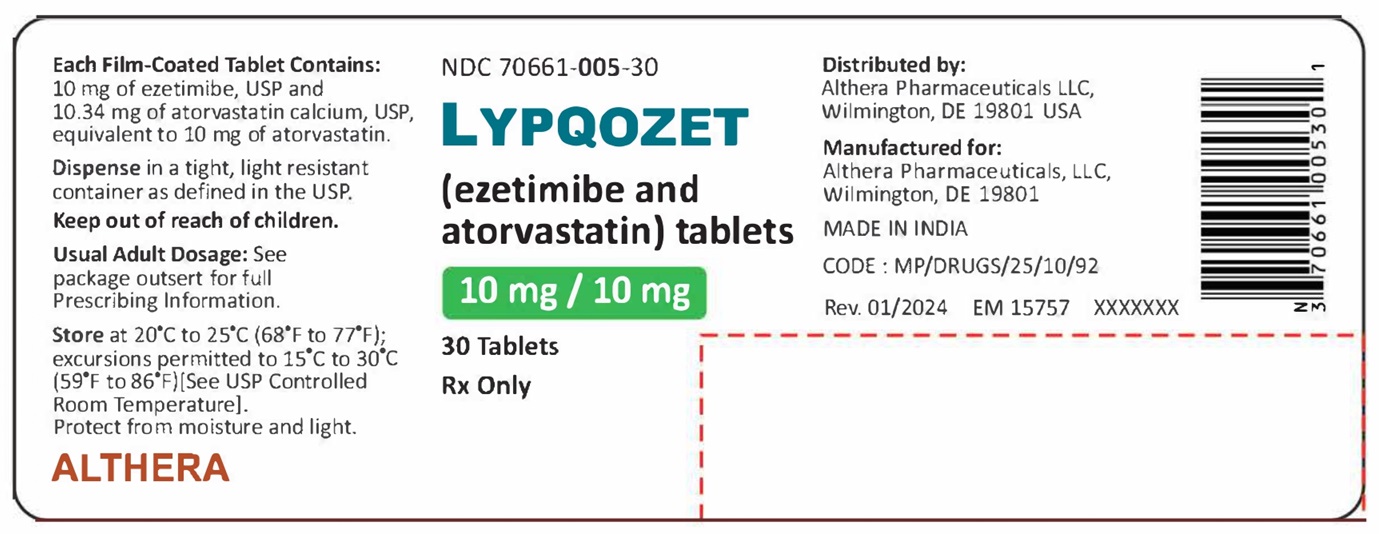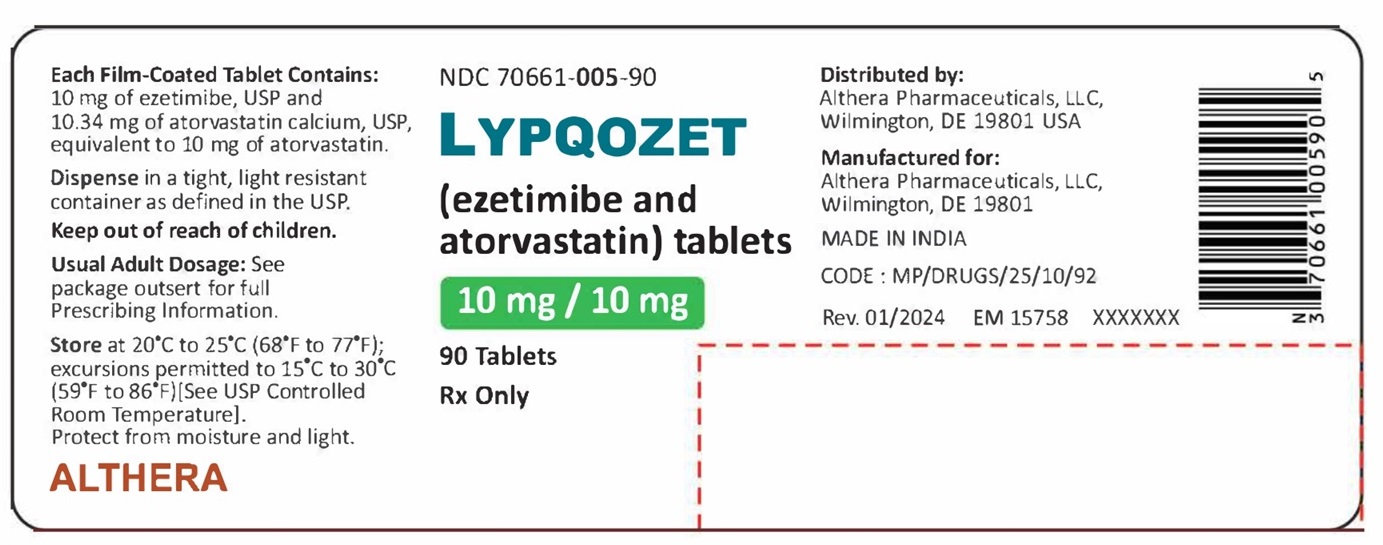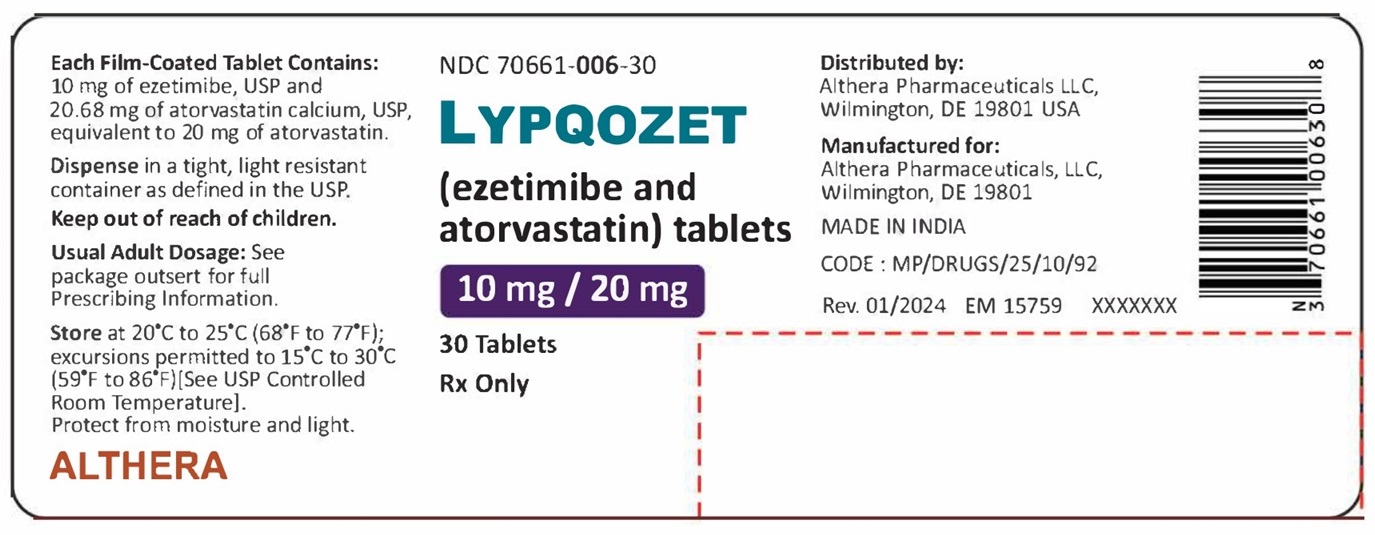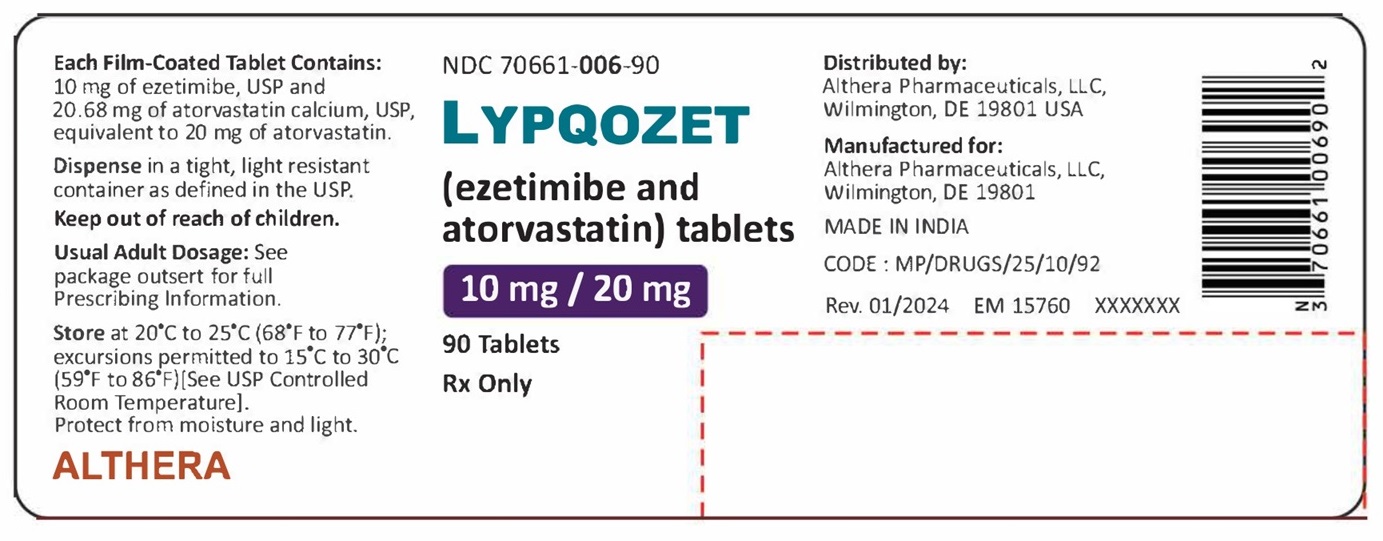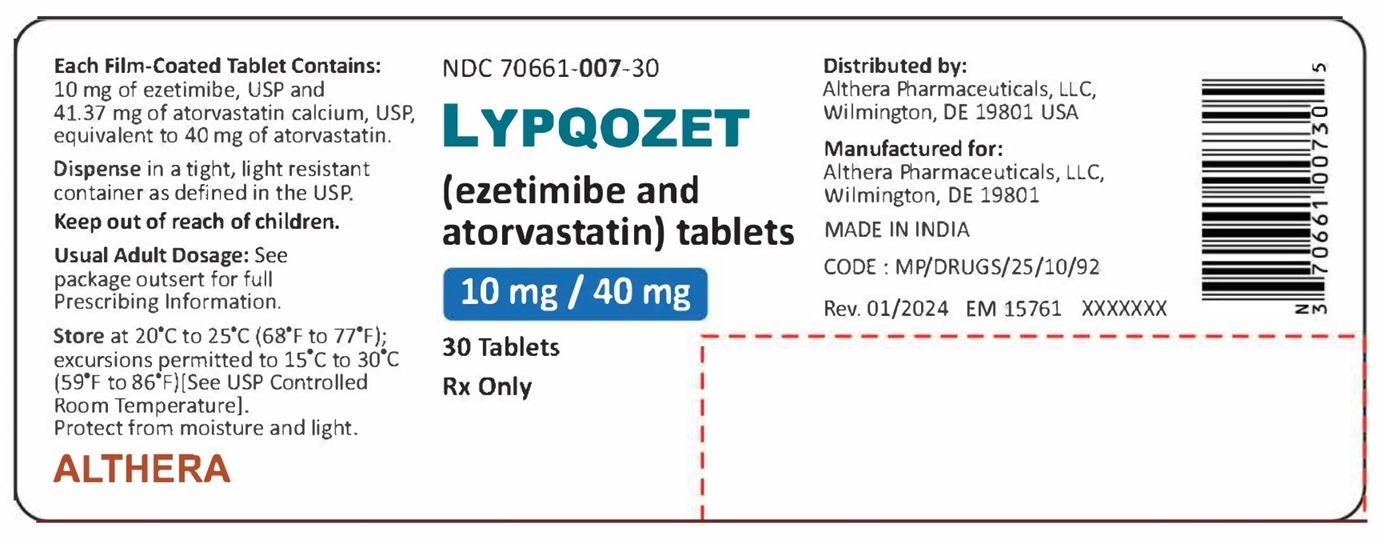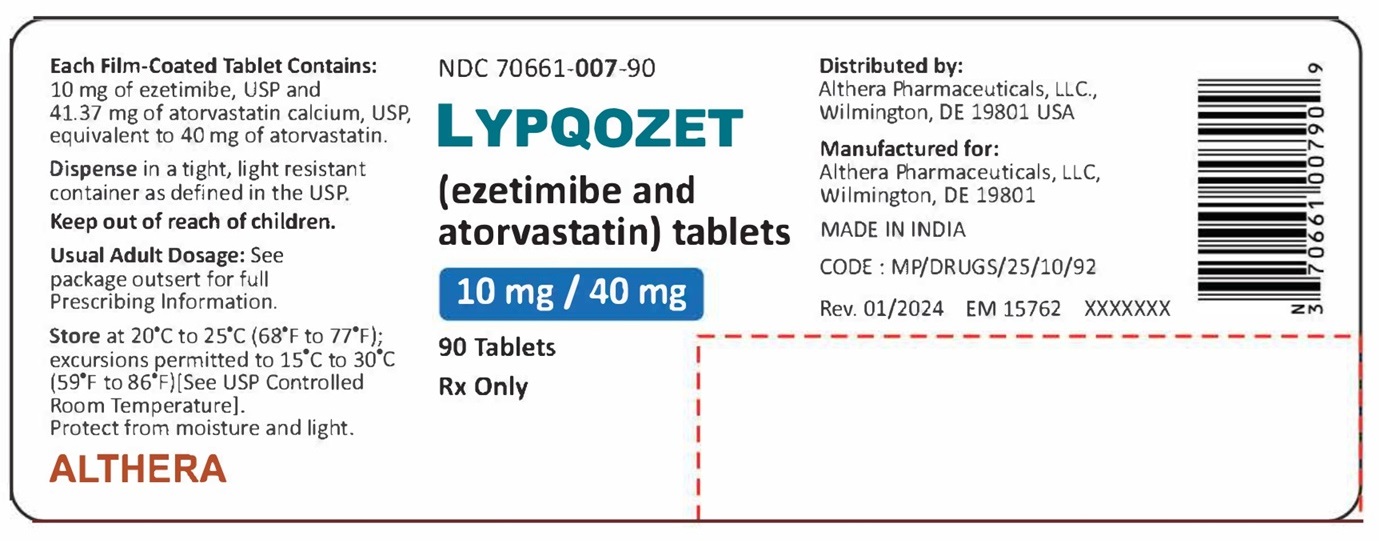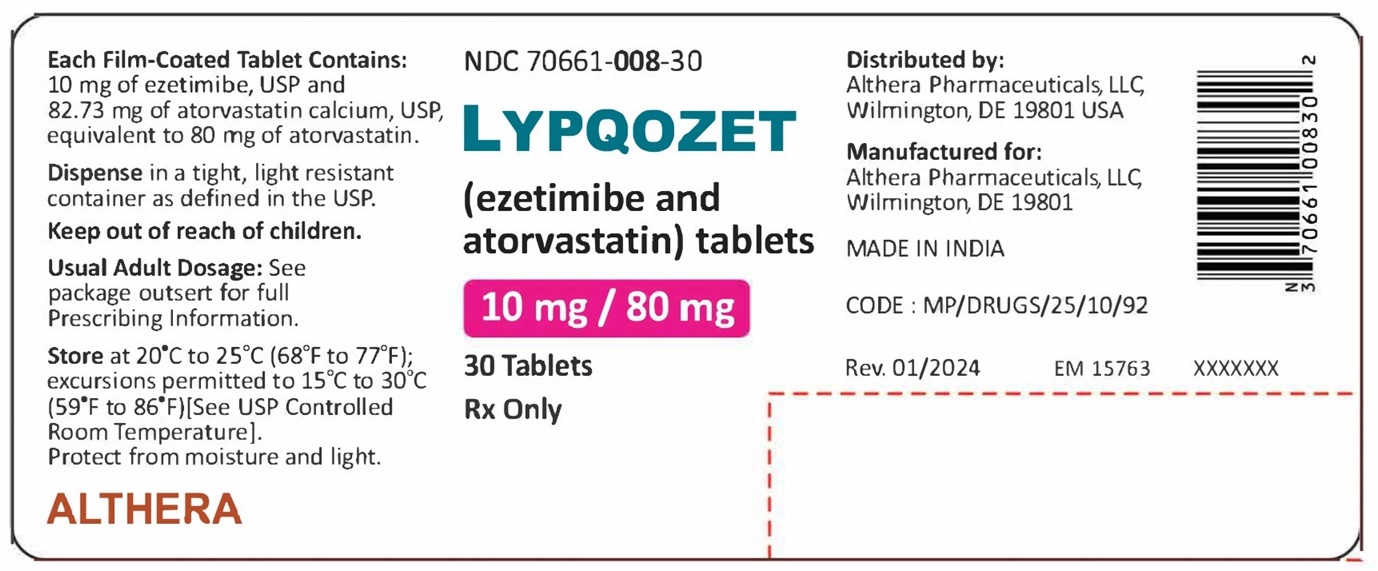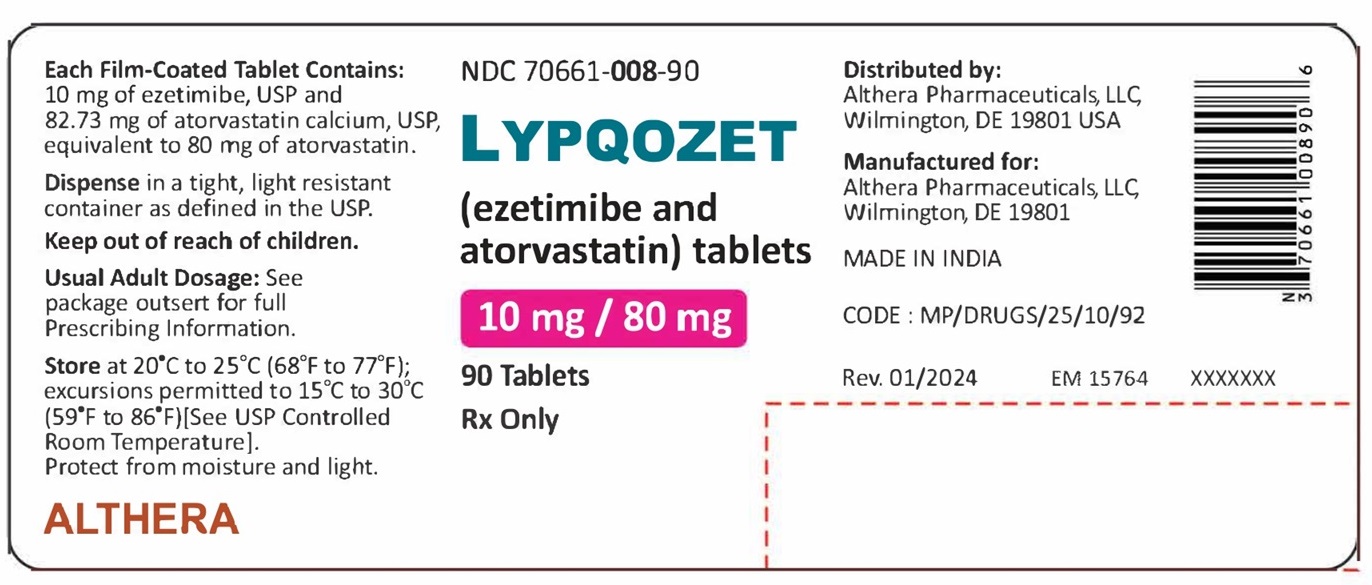 DRUG LABEL: LYPQOZET
NDC: 70661-005 | Form: TABLET
Manufacturer: Althera Pharmaceuticals, LLC
Category: prescription | Type: HUMAN PRESCRIPTION DRUG LABEL
Date: 20240124

ACTIVE INGREDIENTS: EZETIMIBE 10 mg/1 1; ATORVASTATIN CALCIUM TRIHYDRATE 10.34 mg/1 1
INACTIVE INGREDIENTS: CALCIUM CARBONATE; SILICON DIOXIDE; CROSCARMELLOSE SODIUM; HYDROXYPROPYL CELLULOSE, UNSPECIFIED; HYPROMELLOSE, UNSPECIFIED; LACTOSE MONOHYDRATE; MAGNESIUM STEARATE; MICROCRYSTALLINE CELLULOSE; POLYETHYLENE GLYCOL 8000; POLYSORBATE 80; FERRIC OXIDE RED; SODIUM LAURYL SULFATE; TALC; TITANIUM DIOXIDE

HIGHLIGHTS OF PRESCRIBING INFORMATION

These highlights do not include all the information needed to use LYPQOZET safely and effectively. See full prescribing information for LYPQOZET
LYPQOZET® (ezetimibe and atorvastatin) tablets for oral use
Initial U.S. Approval: 2013

RECENT MAJOR CHANGES

Warnings and Precautions
Myopathy/Rhabdomyolysis (5.1) | 09/2020
Immune-Mediated Necrotizing Myopathy (5.2) | 09/2020

1 INDICATIONS AND USAGE

LYPQOZET, which contains a cholesterol absorption inhibitor and an HMG-CoA reductase inhibitor (statin), is indicated as adjunctive therapy to diet to:

- reduce elevated total-C, LDL-C, Apo B, TG, and non-HDL-C, and to increase HDL-C in patients with primary (heterozygous familial and non-familial) hyperlipidemia or mixed hyperlipidemia. (1.1)
- reduce elevated total-C and LDL-C in patients with homozygous familial hypercholesterolemia (HoFH), as an adjunct to other lipid-lowering treatments. (1.2)

Limitations of Use

- No incremental benefit of LYPQOZET on cardiovascular morbidity and mortality over and above that demonstrated for atorvastatin has been established. LYPQOZET has not been studied in Fredrickson Type I, III, IV, and V dyslipidemias. (1.3)

2 DOSAGE AND ADMINISTRATION

- Dosage range is 10/10 mg/day through 10/80 mg/day. (2.1)
- Recommended starting dose is 10/10 mg/day or 10/20 mg/day. (2.1)
- Recommended starting dose is 10/40 mg/day for patients requiring a greater than 55% reduction in LDL-C. (2.1)
- Dosing of LYPQOZET should occur either greater than or equal to 2 hours before or greater than or equal to 4 hours after administration of a bile acid sequestrant. (2.3, 7.12)

3 DOSAGE FORMS AND STRENGTHS

- Tablets (ezetimibe mg/atorvastatin mg): 10/10, 10/20, 10/40, 10/80. (3)

4 CONTRAINDICATIONS

- Active liver disease or unexplained persistent elevations of hepatic transaminase levels. (4, 5.3)
- Hypersensitivity to any component of LYPQOZET. (4, 6.2)
- Women who are pregnant or may become pregnant. (4, 8.1)
- Nursing mothers. (4, 8.3)

5 WARNINGS AND PRECAUTIONS

- Patients should be advised to report promptly any unexplained and/or persistent muscle pain, tenderness, or weakness. LYPQOZET should be discontinued immediately if myopathy is diagnosed or suspected. (5.1)
- Skeletal muscle effects (e. g., myopathy and rhabdomyolysis): Risks increase with higher doses and concomitant use of certain CYP3A4 inhibitors, fibric acid derivatives, and cyclosporine. Predisposing factors include advanced age (>65), uncontrolled hypothyroidism, and renal impairment. Rare cases of rhabdomyolysis with acute renal failure secondary to myoglobinuria have been reported. (5.1, 8.5)
- Immune-Mediated Necrotizing Myopathy (IMNM): There have been rare reports of IMNM, an autoimmune myopathy, associated with statin use. IMNM is characterized by: proximal muscle weakness and elevated serum creatine kinase, which persist despite discontinuation of statin treatment; positive anti-HMG CoA reductase antibody; muscle biopsy showing necrotizing myopathy; and improvement with immunosuppressive agents. (5.2)
- Liver enzyme abnormalities: Persistent elevations in hepatic transaminase can occur. Check liver enzyme tests before initiating therapy and as clinically indicated thereafter. (5.3)

6 ADVERSE REACTIONS

- Common adverse reactions (incidence ≥2% and greater than placebo) are: increased ALT, increased AST, and musculoskeletal pain. (6.1)

To report SUSPECTED ADVERSE REACTIONS, contact Althera at 1-877-495-3908 or FDA at 1-800-FDA-1088 or www.fda.gov/medwatch.

7 DRUG INTERACTIONS

Drug Interactions Associated with Increased Risk of Myopathy/Rhabdomyolysis with Atorvastatin (2.3, 5.1, 7, 12.3)
Interacting Agents | Prescribing Recommendations for LYPQOZET
Cyclosporine, HIV protease inhibitors (tipranavir plus ritonavir), hepatitis C protease inhibitor (telaprevir), gemfibrozil | Avoid LYPQOZET
HIV protease inhibitor (lopinavir plus ritonavir) | Use with caution and lowest dose necessary.
Clarithromycin, itraconazole, HIV protease inhibitors (saquinavir plus ritonavir, darunavir plus ritonavir, fosamprenavir, fosamprenavir plus ritonavir), hepatitis C antiviral agents (elbasvir and grazoprevir) | Do not exceed 10/20 mg LYPQOZET daily.
HIV protease inhibitor (nelfinavir), hepatitis C protease inhibitor (boceprevir) | Do not exceed 10/40 mg LYPQOZET daily.

- Other lipid-lowering medications: Use with fenofibrates or lipid-modifying doses (≥1 g/day) of niacin increases the risk of adverse skeletal muscle effects. Caution should be used when prescribing with LYPQOZET. (7)
- Fenofibrates: Combination increases exposure of ezetimibe. If cholelithiasis is suspected in a patient receiving ezetimibe and a fenofibrate, gallbladder studies are indicated and alternative lipid-lowering therapy should be considered. (7.5, 12.3)
- Cholestyramine: Combination decreases exposure of ezetimibe. (2.3, 12.3)
- Digoxin: Patients should be monitored appropriately. (7.7)
- Oral contraceptives: Values for norethindrone and ethinyl estradiol may be increased. (7.8)
- Rifampin should be simultaneously coadministered with LYPQOZET. (7.10)

8 USE IN SPECIFIC POPULATIONS

- Hepatic impairment: Plasma concentrations of atorvastatin are markedly increased in patients with chronic alcoholic liver disease. (8.6, 12.3)

FULL PRESCRIBING INFORMATION

1 INDICATIONS AND USAGE

Therapy with lipid-altering agents should be only one component of multiple risk factor intervention in individuals at significantly increased risk for atherosclerotic vascular disease due to hypercholesterolemia. Drug therapy is indicated as an adjunct to diet when the response to a diet restricted in saturated fat and cholesterol and other nonpharmacologic measures alone has been inadequate.

1.1 Primary Hyperlipidemia

LYPQOZET is indicated for the reduction of elevated total cholesterol (total-C), low-density lipoprotein cholesterol (LDL-C), apolipoprotein B (Apo B), triglycerides (TG), and non-high-density lipoprotein cholesterol (non-HDL-C), and to increase high-density lipoprotein cholesterol (HDL-C) in patients with primary (heterozygous familial and non-familial) hyperlipidemia or mixed hyperlipidemia.

1.2 Homozygous Familial Hypercholesterolemia (HoFH)

LYPQOZET is indicated for the reduction of elevated total-C and LDL-C in patients with homozygous familial hypercholesterolemia, as an adjunct to other lipid-lowering treatments (e. g., LDL apheresis) or if such treatments are unavailable.

1.3 Limitations of Use

No incremental benefit of LYPQOZET on cardiovascular morbidity and mortality over and above that demonstrated for atorvastatin has been established. LYPQOZET has not been studied in Fredrickson type I, III, IV, and V dyslipidemias.

2 DOSAGE AND ADMINISTRATION

2.1 Recommended Dosing

The dosage range of LYPQOZET is 10/10 mg/day to 10/80 mg/day. The recommended starting dose of LYPQOZET is 10/10 mg/day or 10/20 mg/day. LYPQOZET can be administered as a single dose at any time of the day, with or without food. The recommended starting dose for patients who require a larger reduction in LDL-C (greater than 55%) is 10/40 mg/day. After initiation and/or upon titration of LYPQOZET, lipid levels should be analyzed within 2 or more weeks and dosage adjusted accordingly.

Patients should swallow LYPQOZET tablets whole. Tablets should not be crushed, dissolved, or chewed.

2.2 Patients with Homozygous Familial Hypercholesterolemia

The dosage of LYPQOZET in patients with homozygous familial hypercholesterolemia is 10/40 mg/day or 10/80 mg/day. LYPQOZET should be used as an adjunct to other lipid-lowering treatments (e. g., LDL apheresis) in these patients or if such treatments are unavailable.

2.3 Coadministration with Other Drugs

Bile Acid Sequestrants

Dosing of LYPQOZET should occur either greater than or equal to 2 hours before or greater than or equal to 4 hours after administration of a bile acid sequestrant [see Drug Interactions (7.12)].

Cyclosporine, Clarithromycin, Itraconazole, or Certain HIV/HCV Antiviral Agents

In patients taking cyclosporine or the HIV protease inhibitors (tipranavir plus ritonavir) or the hepatitis C protease inhibitor (telaprevir), therapy with LYPQOZET should be avoided. In patients with HIV taking lopinavir plus ritonavir, caution should be used when prescribing LYPQOZET and the lowest dose necessary employed. In patients taking clarithromycin, itraconazole, or in patients with HIV taking a combination of saquinavir plus ritonavir, darunavir plus ritonavir, fosamprenavir, or fosamprenavir plus ritonavir, therapy with LYPQOZET should be limited to 10/20 mg, and appropriate clinical assessment is recommended to ensure that the lowest dose necessary of LYPQOZET is employed. In patients taking hepatitis C antiviral agents containing elbasvir and grazoprevir, therapy with LYPQOZET should not exceed 10/20 mg. In patients taking the HIV protease inhibitor nelfinavir or the hepatitis C protease inhibitor boceprevir, therapy with LYPQOZET should be limited to 10/40 mg, and appropriate clinical assessment is recommended to ensure that the lowest dose necessary of LYPQOZET is employed [see Warnings and Precautions (5.1) and Drug Interactions (7)].

Other Concomitant Lipid-Lowering Therapy

The combination of LYPQOZET and gemfibrozil is not recommended [see Warnings and Precautions (5.1) and Drug Interactions (7.4)].

3 DOSAGE FORMS AND STRENGTHS

LYPQOZET is available as follows:
10 mg/10 mg - White to off white, oval shaped film-coated tablets, debossed with “W 10” on one side and plain on other side containing 10 mg of ezetimibe, USP and 10.34 mg of atorvastatin calcium, USP, equivalent to 10 mg of atorvastatin.

10 mg/20 mg - White to off white, oval shaped film-coated tablets, debossed with “W 20” on one side and plain on other side containing 10 mg of ezetimibe, USP and 20.68 mg of atorvastatin calcium, USP, equivalent to 20 mg of atorvastatin.

10 mg/40 mg - White to off white, oval shaped film-coated tablets, debossed with “W 40” on one side and plain on other side containing 10 mg of ezetimibe, USP and 41.37 mg of atorvastatin calcium, USP, equivalent to 40 mg of atorvastatin.

10 mg/80 mg - White to off white, oval shaped film-coated tablets, debossed with “W 80” on one side and plain on other side containing 10 mg of ezetimibe, USP and 82.73 mg of atorvastatin calcium, USP, equivalent to 80 mg of atorvastatin.

4 CONTRAINDICATIONS

Active liver disease or unexplained persistent elevations of hepatic transaminase levels.

Hypersensitivity to any component of ezetimibe and atorvastatin tablets [see Adverse Reactions (6.2)].

Women who are pregnant or may become pregnant. Ezetimibe and atorvastatin tablets may cause fetal harm when administered to a pregnant woman. Serum cholesterol and triglycerides increase during normal pregnancy, and cholesterol or cholesterol derivatives are essential for fetal development. Atherosclerosis is a chronic process and discontinuation of lipid-lowering drugs during pregnancy should have little impact on the outcome of long-term therapy of primary hypercholesterolemia. There are no adequate and well-controlled studies of ezetimibe and atorvastatin tablets use during pregnancy; however in rare reports, congenital anomalies were observed following intrauterine exposure to statins. In rat and rabbit animal reproduction studies, atorvastatin revealed no evidence of teratogenicity. Ezetimibe and atorvastatin tablets should be administered to women of childbearing age only when such patients are highly unlikely to conceive and have been informed of the potential hazards. If the patient becomes pregnant while taking this drug, ezetimibe and atorvastatin tablets should be discontinued immediately, and the patient should be apprised of the potential hazard to the fetus [see Use in Specific Populations (8.1)].

Nursing mothers. It is not known whether atorvastatin is excreted into human milk; however, a small amount of another drug in this class does pass into breast milk. Because statins have the potential for serious adverse reactions in nursing infants, women who require ezetimibe and atorvastatin tablets treatment should not breastfeed their infants [see Use in Specific Populations (8.3)].

5 WARNINGS AND PRECAUTIONS

5.1 Myopathy/Rhabdomyolysis

Atorvastatin
Rare cases of rhabdomyolysis with acute renal failure secondary to myoglobinuria have been reported with atorvastatin and with other drugs in this class. A history of renal impairment may be a risk factor for the development of rhabdomyolysis. Such patients merit closer monitoring for skeletal muscle effects.

Atorvastatin, like other statins, occasionally causes myopathy, defined as muscle aches or muscle weakness in conjunction with increases in creatine phosphokinase (CPK) values >10 times upper limit of normal (ULN). The concomitant use of higher doses of atorvastatin with certain drugs such as cyclosporine and strong CYP3A4 inhibitors (e. g., clarithromycin, itraconazole, and HIV protease inhibitors) increases the risk of myopathy/rhabdomyolysis.

Myopathy should be considered in any patient with diffuse myalgias, muscle tenderness or weakness, and/or marked elevation of CPK. Patients should be advised to report promptly unexplained muscle pain, tenderness or weakness, particularly if accompanied by malaise or fever or if muscle signs and symptoms persist after discontinuing ezetimibe and atorvastatin tablets. Ezetimibe and atorvastatin tablets therapy should be discontinued if markedly elevated CPK levels occur or myopathy is diagnosed or suspected.

The risk of myopathy during treatment with statins is increased with concurrent administration of cyclosporine, fibric acid derivatives, erythromycin, clarithromycin, the hepatitis C antiviral agents telaprevir, a combination of elbasvir plus grazoprevir, combinations of HIV protease inhibitors, including saquinavir plus ritonavir, lopinavir plus ritonavir, tipranavir plus ritonavir, darunavir plus ritonavir, fosamprenavir, and fosamprenavir plus ritonavir, niacin, or azole antifungals. Physicians considering combined therapy with ezetimibe and atorvastatin tablets and fibric acid derivatives, erythromycin, clarithromycin, a combination of elbasvir plus grazoprevir, a combination of saquinavir plus ritonavir, lopinavir plus ritonavir, darunavir plus ritonavir, fosamprenavir, or fosamprenavir plus ritonavir, azole antifungals, or lipid-modifying doses of niacin should carefully weigh the potential benefits and risks and should carefully monitor patients for any signs or symptoms of muscle pain, tenderness, or weakness, particularly during the initial months of therapy and during any periods of upward dosage titration of either drug. Lower starting and maintenance doses of ezetimibe and atorvastatin tablets should be considered when taken concomitantly with the aforementioned drugs [see Drug Interactions (7)]. Periodic CPK determinations may be considered in such situations, but there is no assurance that such monitoring will prevent the occurrence of severe myopathy.

Prescribing recommendations for interacting agents are summarized in Table 1 [see also Dosage and Administration (2.3), Drug Interactions (7), Clinical Pharmacology (12.3)].

Table 1: Drug Interactions Associated with Increased Risk of Myopathy/Rhabdomyolysis with Atorvastatin
Interacting Agents | Prescribing Recommendations for Ezetimibe and Atorvastatin Tablets
Cyclosporine, HIV protease inhibitors (tipranavir plus ritonavir), hepatitis C protease inhibitor (telaprevir), gemfibrozil | Avoid ezetimibe and atorvastatin tablets.
HIV protease inhibitor (lopinavir plus ritonavir) | Use with caution and lowest dose necessary.
Clarithromycin, itraconazole, HIV protease inhibitors (saquinavir plus ritonavir*, darunavir plus ritonavir, fosamprenavir, fosamprenavir plus ritonavir), hepatitis C antiviral agents (elbasvir and grazoprevir) | Do not exceed 10/20 mg ezetimibe and atorvastatin tablets daily.
HIV protease inhibitor (nelfinavir), hepatitis C protease inhibitor (boceprevir) | Do not exceed 10/40 mg ezetimibe and atorvastatin tablets daily.

*Use with caution and with the lowest dose necessary [see Clinical Pharmacology (12.3)]

Cases of myopathy, including rhabdomyolysis, have been reported with atorvastatin coadministered with colchicine, and caution should be exercised when prescribing ezetimibe and atorvastatin tablets with colchicine [see Drug Interactions (7.11)].

Ezetimibe and atorvastatin tablets therapy should be temporarily withheld or discontinued in any patient with an acute, serious condition suggestive of a myopathy or having a risk factor predisposing to the development of renal failure secondary to rhabdomyolysis (e. g., severe acute infection, hypotension, major surgery, trauma, severe metabolic, endocrine and electrolyte disorders, and uncontrolled seizures).

Ezetimibe
In clinical trials, there was no excess of myopathy or rhabdomyolysis associated with ezetimibe compared with the relevant control arm (placebo or statin alone). However, myopathy and rhabdomyolysis are known adverse reactions to statins and other lipid-lowering drugs. In clinical trials, the incidence of creatine phosphokinase (CPK) >10 times ULN was 0.2% for ezetimibe vs. 0.1% for placebo, and 0.1% for ezetimibe coadministered with a statin vs. 0.4% for statins alone. Risk for skeletal muscle toxicity increases with higher doses of statin, advanced age (>65), hypothyroidism, renal impairment, and depending on the statin used, concomitant use of other drugs.

In postmarketing experience with ezetimibe, cases of myopathy and rhabdomyolysis have been reported. Most patients who developed rhabdomyolysis were taking a statin prior to initiating ezetimibe. However, rhabdomyolysis has been reported with ezetimibe monotherapy and with the addition of ezetimibe to agents known to be associated with increased risk of rhabdomyolysis, such as fibric acid derivatives. Ezetimibe and atorvastatin tablets and a fenofibrate, if taking concomitantly, should both be immediately discontinued if myopathy is diagnosed or suspected. The presence of muscle symptoms and a CPK level >10 times the ULN indicates myopathy.

5.2 Immune-Mediated Necrotizing Myopathy

There have been rare reports of immune-mediated necrotizing myopathy (IMNM), an autoimmune myopathy, associated with statin use. IMNM is characterized by: proximal muscle weakness and elevated serum creatine kinase, which persist despite discontinuation of statin treatment; positive anti-HMG CoA reductase antibody; muscle biopsy showing necrotizing myopathy; and improvement with immunosuppressive agents. Additional neuromuscular and serologic testing may be necessary. Treatment with immunosuppressive agents may be required. Consider risk of IMNM carefully prior to initiation of a different statin. If therapy is initiated with a different statin, monitor for signs and symptoms of IMNM.

5.3 Liver Enzymes

Atorvastatin
Statins, like some other lipid-lowering therapies, have been associated with biochemical abnormalities of liver function. Persistent elevations (>3 times ULN occurring on 2 or more occasions) in serum transaminases occurred in 0.7% of patients who received atorvastatin in clinical trials. The incidence of these abnormalities was 0.2%, 0.2%, 0.6%, and 2.3% for 10, 20, 40, and 80 mg atorvastatin, respectively.

One patient in clinical trials of atorvastatin developed jaundice. Increases in liver function tests (LFT) in other patients were not associated with jaundice or other clinical signs or symptoms. Upon dose reduction, drug interruption, or discontinuation, transaminase levels returned to or near pretreatment levels without sequelae. Eighteen of 30 patients with persistent LFT elevations continued treatment with a reduced dose of atorvastatin.

Ezetimibe
In controlled clinical studies, the incidence of consecutive elevations (≥3 times ULN) in hepatic transaminase levels was similar between ezetimibe (0.5%) and placebo (0.3%).

In controlled clinical combination studies of ezetimibe coadministered with atorvastatin, the incidence of consecutive elevations (≥3 times ULN) in hepatic transaminase levels was 0.6% for patients treated with ezetimibe administered with atorvastatin. These elevations in transaminases were generally asymptomatic, not associated with cholestasis, and returned to baseline after discontinuation of therapy or with continued treatment.

Ezetimibe and Atorvastatin Tablets
It is recommended that liver enzyme tests be obtained prior to initiating therapy with ezetimibe and atorvastatin tablets and repeated as clinically indicated. There have been rare postmarketing reports of fatal and non-fatal hepatic failure in patients taking statins, including atorvastatin. If serious liver injury with clinical symptoms and/or hyperbilirubinemia or jaundice occurs during treatment with ezetimibe and atorvastatin tablets, promptly interrupt therapy. If an alternate etiology is not found, do not restart ezetimibe and atorvastatin tablets.

Ezetimibe and atorvastatin tablets should be used with caution in patients who consume substantial quantities of alcohol and/or have a history of liver disease. Active liver disease or unexplained persistent transaminase elevations are contraindications to the use of ezetimibe and atorvastatin tablets [see Contraindications (4)].

5.4 Endocrine Function

Increases in HbA1c and fasting serum glucose levels have been reported with HMG-CoA reductase inhibitors, including atorvastatin.

Statins interfere with cholesterol synthesis and theoretically might blunt adrenal and/or gonadal steroid production. Clinical studies have shown that atorvastatin does not reduce basal plasma cortisol concentration or impair adrenal reserve and that ezetimibe did not impair adrenocortical steroid hormone production. The effects of statins on male fertility have not been studied in adequate numbers of patients. The effects, if any, on the pituitary-gonadal axis in premenopausal women are unknown. Caution should be exercised if ezetimibe and atorvastatin tablets are administered concomitantly with drugs that may decrease the levels or activity of endogenous steroid hormones, such as ketoconazole, spironolactone, and cimetidine.

5.5 Use in Patients with Recent Stroke or TIA

In a post-hoc analysis of the Stroke Prevention by Aggressive Reduction in Cholesterol Levels (SPARCL) study where atorvastatin 80 mg vs. placebo was administered in 4,731 subjects without CHD who had a stroke or TIA within the preceding 6 months, a higher incidence of hemorrhagic stroke was seen in the atorvastatin 80 mg group compared to placebo (55, 2.3% atorvastatin vs. 33, 1.4% placebo; HR: 1.68, 95% CI: 1.09, 2.59; p=0.0168). The incidence of fatal hemorrhagic stroke was similar across treatment groups (17 vs. 18 for the atorvastatin and placebo groups, respectively). The incidence of nonfatal hemorrhagic stroke was significantly higher in the atorvastatin (38, 1.6%) group as compared to the placebo group (16, 0.7%). Some baseline characteristics, including hemorrhagic and lacunar stroke on study entry, were associated with a higher incidence of hemorrhagic stroke in the atorvastatin group.

5.6 CNS Toxicity

Atorvastatin
Brain hemorrhage was seen in a female dog treated for 3 months at 120 mg/kg/day. Brain hemorrhage and optic nerve vacuolation were seen in another female dog that was sacrificed in moribund condition after 11 weeks of escalating doses up to 280 mg/kg/day. The 120 mg/kg dose resulted in a systemic exposure approximately 16 times the human plasma area-under-the-curve (AUC, 0-24 hours) based on the maximum human dose of 80 mg/day. A single tonic convulsion was seen in each of 2 male dogs (one treated at 10 mg/kg/day and one at 120 mg/kg/day) in a 2-year study. No CNS lesions have been observed in mice after chronic treatment for up to 2 years at doses up to 400 mg/kg/day or in rats at doses up to 100 mg/kg/day. These doses were 6 to 11 times (mouse) and 8 to 16 times (rat) the human AUC(0-24) based on the maximum recommended human dose of 80 mg/day.

CNS vascular lesions, characterized by perivascular hemorrhages, edema, and mononuclear cell infiltration of perivascular spaces, have been observed in dogs treated with other members of this class. A chemically similar drug in this class produced optic nerve degeneration (Wallerian degeneration of retinogeniculate fibers) in clinically normal dogs in a dose-dependent fashion at a dose that produced plasma drug levels about 30 times higher than the mean drug level in humans taking the highest recommended dose.

6 ADVERSE REACTIONS

The following serious adverse reactions are discussed in greater detail in other sections of the label:

- Rhabdomyolysis and myopathy [see Warnings and Precautions (5.1)]
- Liver enzyme abnormalities [see Warnings and Precautions (5.3)]

6.1 Clinical Trials Experience

Ezetimibe and Atorvastatin Tablets
Because clinical studies are conducted under widely varying conditions, adverse reaction rates observed in the clinical studies of a drug cannot be directly compared to rates in the clinical studies of another drug and may not reflect the rates observed in clinical practice.

In an ezetimibe and atorvastatin tablets placebo-controlled clinical trial, 628 patients (age range 18 to 86 years, 59% women, 85% Caucasians, 6% Blacks, 5% Hispanics, 3% Asians) with a median treatment duration of 12 weeks, 6% of patients on ezetimibe and atorvastatin tablets and 5% of patients on placebo discontinued due to adverse reactions.

The most common adverse reactions in the group treated with ezetimibe and atorvastatin tablets that led to treatment discontinuation and occurred at a rate greater than placebo were:

- Myalgia (0.8%)
- Abdominal pain (0.8%)
- Increased hepatic enzymes (0.8%)

The most commonly reported adverse reactions (incidence ≥2% and greater than placebo) in this trial were: increased ALT (5%), increased AST (4%), and musculoskeletal pain (4%).

Ezetimibe and atorvastatin tablets have been evaluated for safety in 2403 patients in 7 clinical trials (one placebo-controlled trial and six active-controlled trials).

Table 2 summarizes the frequency of clinical adverse reactions reported in ≥2% of patients treated with ezetimibe and atorvastatin tablets (n=255) and at an incidence greater than placebo, regardless of causality assessment, from the placebo-controlled trial.

Table 2*: Clinical and Selected Laboratory Adverse Reactions Occurring in ≥2% of Patients Treated with Ezetimibe and Atorvastatin Tablets and at an Incidence Greater than Placebo, Regardless of Causality
Body System/Organ Class; Adverse Reaction | Placebo; (%); n=60 | Ezetimibe; 10 mg; (%); n=65 | Atorvastatin†; (%); n=248 | Ezetimibe and Atorvastatin Tablets†; (%); n=255
Nervous system disorders
Dizziness | 0 | 6 | <1 | 2
Respiratory, thoracic, and mediastinal disorders
Coughing | 0 | 3 | <1 | 2
Gastrointestinal disorders
Abdominal pain | 2 | 2 | 4 | 3
Nausea | 0 | 2 | 5 | 3
Musculoskeletal and connective tissue disorders
Arthralgia | 0 | 5 | 6 | 3
Muscle weakness | 0 | 2 | 0 | 2
Musculoskeletal pain | 3 | 8 | 5 | 4
Metabolism and nutrition disorders
Hyperkalemia | 0 | 0 | <1 | 2
Infections and infestations
Bronchitis | 0 | 2 | 2 | 2
Sinusitis | 0 | 3 | 2 | 2
Vascular disorders
Hot flushes | 0 | 0 | <1 | 2
Investigations
ALT increased | 0 | 0 | 2 | 5
AST increased | 0 | 0 | <1 | 4

* Placebo-controlled combination study in which the active ingredients equivalent to ezetimibe and atorvastatin tablets were coadministered.
† All doses.

After completing the 12-week study, eligible patients were assigned to coadministered ezetimibe and atorvastatin equivalent to ezetimibe and atorvastatin tablets (10/10 to 10/80) or atorvastatin (10 to 80 mg/day) for an additional 48 weeks. The long-term coadministration of ezetimibe plus atorvastatin had an overall safety profile similar to that of atorvastatin alone.

Ezetimibe
In 10 double-blind, placebo-controlled clinical trials, 2396 patients with primary hyperlipidemia (age range 9 to 86 years, 50% women, 90% Caucasians, 5% Blacks, 3% Hispanics, 2% Asians) and elevated LDL-C were treated with ezetimibe 10 mg/day for a median treatment duration of 12 weeks (range 0 to 39 weeks).

Adverse reactions reported in ≥2% of patients treated with ezetimibe and at an incidence greater than placebo regardless of causality assessment are shown in Table 3.

Table 3: Clinical Adverse Reactions Occurring in ≥2% of Patients Treated with Ezetimibe and at an Incidence Greater than Placebo, Regardless of Causality
Body System/Organ Class; Adverse Reaction | Ezetimibe 10 mg (%); n=2396 | Placebo (%); n=1159
Gastrointestinal disorders
Diarrhea | 4.1 | 3.7
General disorders and administration site conditions
Fatigue | 2.4 | 1.5
Infections and infestations
Influenza | 2.0 | 1.5
Sinusitis | 2.8 | 2.2
Upper respiratory tract infection | 4.3 | 2.5
Musculoskeletal and connective tissue disorders
Arthralgia | 3.0 | 2.2
Pain in extremity | 2.7 | 2.5

Atorvastatin
In an atorvastatin placebo-controlled clinical trial database of 16,066 patients (8755 atorvastatin vs. 7311 placebo; age range 10 to 93 years, 39% women, 91% Caucasians, 3% Blacks, 2% Asians, 4% other) with a median treatment duration of 53 weeks, 9.7% of patients on atorvastatin and 9.5% of the patients on placebo discontinued due to adverse reactions regardless of causality.

The most commonly reported adverse reactions (incidence ≥2% and greater than placebo) regardless of causality, in patients treated with atorvastatin in placebo controlled trials (n=8755) were: nasopharyngitis (8.3%), arthralgia (6.9%), diarrhea (6.8%), pain in extremity (6.0%), and urinary tract infection (5.7%).

Table 4 summarizes the frequency of clinical adverse reactions, regardless of causality, reported in ≥2% and at a rate greater than placebo in patients treated with atorvastatin (n=8755), from seventeen placebo-controlled trials.

Table 4: Clinical Adverse Reactions Occurring in >2% in Patients Treated with any dose of Atorvastatin and at an Incidence Greater than Placebo Regardless of Causality (% of patients).
Adverse Reaction* | Any Dose; n=8755 | Atorvastatin; 10 mg; n=3908 | Atorvastatin; 20 mg; n=188 | Atorvastatin; 40 mg; n=604 | Atorvastatin; 80 mg; n=4055 | Placebo; n=7311
Nasopharyngitis | 8.3 | 12.9 | 5.3 | 7.0 | 4.2 | 8.2
Arthralgia | 6.9 | 8.9 | 11.7 | 10.6 | 4.3 | 6.5
Diarrhea | 6.8 | 7.3 | 6.4 | 14.1 | 5.2 | 6.3
Pain in extremity | 6.0 | 8.5 | 3.7 | 9.3 | 3.1 | 5.9
Urinary tract infection | 5.7 | 6.9 | 6.4 | 8.0 | 4.1 | 5.6
Dyspepsia | 4.7 | 5.9 | 3.2 | 6.0 | 3.3 | 4.3
Nausea | 4.0 | 3.7 | 3.7 | 7.1 | 3.8 | 3.5
Musculoskeletal pain | 3.8 | 5.2 | 3.2 | 5.1 | 2.3 | 3.6
Muscle spasms | 3.6 | 4.6 | 4.8 | 5.1 | 2.4 | 3.0
Myalgia | 3.5 | 3.6 | 5.9 | 8.4 | 2.7 | 3.1
Insomnia | 3.0 | 2.8 | 1.1 | 5.3 | 2.8 | 2.9
Pharyngolaryngeal pain | 2.3 | 3.9 | 1.6 | 2.8 | 0.7 | 2.1

*Adverse Reaction >2% in any dose greater than placebo

6.2 Postmarketing Experience

Because the reactions below are reported voluntarily from a population of uncertain size, it is generally not possible to reliably estimate their frequency or establish a causal relationship to drug exposure.

The additional events described below have been identified during post-approval use of ezetimibe and/or atorvastatin.

Blood and lymphatic system disorders: thrombocytopenia

Nervous system disorders: headache; dizziness; paresthesia; peripheral neuropathy

There have been rare postmarketing reports of cognitive impairment (e. g., memory loss, forgetfulness, amnesia, memory impairment, confusion) associated with statin use. These cognitive issues have been reported for all statins. The reports are generally nonserious, and reversible upon statin discontinuation, with variable times to symptom onset (1 day to years) and symptom resolution (median of 3 weeks).

Gastrointestinal disorders: pancreatitis

Skin and subcutaneous tissue disorders: angioedema; bullous rashes (including erythema multiforme, Stevens-Johnson syndrome, and toxic epidermal necrolysis); rash; urticaria

Musculoskeletal and connective tissue disorders: myositis; myopathy/rhabdomyolysis [see Warnings and Precautions (5.1)]

There have been rare reports of immune-mediated necrotizing myopathy associated with statin use [see Warnings and Precautions (5.1)].

Injury, poisoning and procedural complications: tendon rupture

Immune system disorders: anaphylaxis; hypersensitivity reactions

Hepatobiliary disorders: hepatitis; cholelithiasis; cholecystitis; fatal and nonfatal hepatic failure

Psychiatric disorders: depression

Respiratory: interstitial lung disease

Laboratory abnormalities: elevated creatine phosphokinase

General disorders and administration site conditions: fatigue

7 DRUG INTERACTIONS

[See Clinical Pharmacology (12.3).]

LYPQOZET
The risk of myopathy during treatment with statins is increased with concurrent administration of fibric acid derivatives, lipid-modifying doses of niacin, cyclosporine, or strong CYP3A4 inhibitors (e. g., clarithromycin, HIV protease inhibitors, and itraconazole) [see Warnings and Precautions (5.1) and Clinical Pharmacology (12.3)].

7.1 Strong Inhibitors of Cytochrome P450 3A4

Atorvastatin is metabolized by cytochrome P450 3A4. Concomitant administration of atorvastatin with strong inhibitors of CYP3A4 can lead to increases in plasma concentrations of atorvastatin. The extent of interaction and potentiation of effects depend on the variability of effect on CYP3A4. Because LYPQOZET contains atorvastatin, the risk of myopathy during treatment with LYPQOZET is increased with concurrent administration of:

Clarithromycin: Atorvastatin AUC was significantly increased with concomitant administration of 80 mg atorvastatin with clarithromycin (500 mg twice daily) compared to that of atorvastatin alone [see Clinical Pharmacology (12.3)]. Therefore, in patients taking clarithromycin, caution should be used when the LYPQOZET dose exceeds 10/20 mg [see Warnings and Precautions (5.1) and Dosage and Administration (2.3)].

Combination of Protease Inhibitors: Atorvastatin AUC was significantly increased with concomitant administration of atorvastatin with several combinations of HIV protease inhibitors, as well as with the hepatitis C protease inhibitor telaprevir, compared to that of atorvastatin alone [see Clinical Pharmacology (12.3)]. Therefore, in patients taking the HIV protease inhibitor tipranavir plus ritonavir, or the hepatitis C protease inhibitor telaprevir, concomitant use of LYPQOZET should be avoided. In patients taking the HIV protease inhibitor lopinavir plus ritonavir, caution should be used when prescribing LYPQOZET and the lowest dose necessary should be used. In patients taking the HIV protease inhibitors saquinavir plus ritonavir, darunavir plus ritonavir, fosamprenavir, or fosamprenavir plus ritonavir, the dose of LYPQOZET should not exceed 10/20 mg and should be used with caution [see Warnings and Precautions (5.1) and Dosage and Administration (2.3)]. In patients taking the HIV protease inhibitor nelfinavir or the hepatitis C protease inhibitor boceprevir, the dose of LYPQOZET should not exceed 10/40 mg daily and close clinical monitoring is recommended.

Itraconazole: Atorvastatin AUC was significantly increased with concomitant administration of atorvastatin 40 mg and itraconazole 200 mg [see Clinical Pharmacology (12.3)]. Therefore, in patients taking itraconazole, do not use a LYPQOZET dose that exceeds 10/20 mg [see Warnings and Precautions (5.1) and Dosage and Administration (2.3)].

7.2 Cyclosporine

Atorvastatin and atorvastatin-metabolites are substrates of the OATP1B1 transporter. Inhibitors of the OATP1B1 (e. g., cyclosporine) can increase the bioavailability of atorvastatin. Atorvastatin AUC was significantly increased with concomitant administration of atorvastatin 10 mg and cyclosporine 5.2 mg/kg/day compared to that of atorvastatin alone [see Clinical Pharmacology (12.3)].

In addition, ezetimibe and cyclosporine used concomitantly can increase exposure to both ezetimibe and cyclosporine. The degree of increase in ezetimibe exposure may be greater in patients with severe renal impairment.

The coadministration of LYPQOZET with cyclosporine should be avoided [see Warnings and Precautions (5.1)].

7.3 Grapefruit Juice

Grapefruit juice contains one or more components that inhibit CYP3A4 and can increase plasma concentrations of atorvastatin, especially with excessive grapefruit juice consumption (>1.2 liters per day).

7.4 Gemfibrozil

Due to an increased risk of myopathy/rhabdomyolysis when HMG-CoA reductase inhibitors are coadministered with gemfibrozil, concomitant administration of LYPQOZET with gemfibrozil should be avoided [see Warnings and Precautions (5.1)].

7.5 Fenofibrates (e. g., fenofibrate and fenofibric acid)

Because it is known that the risk of myopathy during treatment with HMG-CoA reductase inhibitors is increased with concurrent administration of fenofibrates, LYPQOZET should be administered with caution when used concomitantly with a fenofibrate [see Warnings and Precautions (5.1)].

Fenofibrates may increase cholesterol excretion into the bile, leading to cholelithiasis. If cholelithiasis is suspected in a patient receiving LYPQOZET and a fenofibrate, gallbladder studies are indicated and alternative lipid-lowering therapy should be considered [see the product labeling for fenofibrate and fenofibric acid].

7.6 Niacin

The risk of skeletal muscle effects may be enhanced when LYPQOZET is used in combination with niacin; a reduction in LYPQOZET dosage should be considered in this setting [see Warnings and Precautions (5.1)].

7.7 Digoxin

When multiple doses of atorvastatin and digoxin were coadministered, steady state plasma digoxin concentrations increased by approximately 20%. Patients taking digoxin should be monitored appropriately.

7.8 Oral Contraceptives

Coadministration of atorvastatin and an oral contraceptive increased AUC values for norethindrone and ethinyl estradiol [see Clinical Pharmacology (12.3)]. These increases should be considered when selecting an oral contraceptive for a woman taking LYPQOZET.

7.9 Elbasvir and Grazoprevir

Concomitant administration of elbasvir and grazoprevir may lead to increased plasma concentrations of atorvastatin and an increased risk of myopathy; therefore, a dose adjustment of atorvastatin may be necessary. Coadministration of elbasvir and grazoprevir with atorvastatin increases plasma concentrations of atorvastatin by 1.9-fold due in part to BCRP and/or CYP3A, OATP1B1 inhibition; therefore, the dose of LYPQOZET should not exceed 10/20 mg daily in patients receiving concomitant medication with products containing elbasvir and grazoprevir [see Dosage and Administration (2.3), Warnings and Precautions (5.1), and Clinical Pharmacology (12.3)].

7.10 Rifampin or Other Inducers of Cytochrome P450 3A4

Concomitant administration of atorvastatin with inducers of cytochrome P450 3A4 (e. g., efavirenz, rifampin) can lead to variable reductions in plasma concentrations of atorvastatin. Due to the dual interaction mechanism of rifampin, simultaneous coadministration of LYPQOZET with rifampin is recommended, as delayed administration of atorvastatin after administration of rifampin has been associated with a significant reduction in atorvastatin plasma concentrations.

7.11 Colchicine

Cases of myopathy, including rhabdomyolysis, have been reported with atorvastatin coadministered with colchicine, and caution should be exercised when prescribing LYPQOZET with colchicine.

7.12 Cholestyramine

Concomitant cholestyramine administration decreased the mean area under the curve (AUC) of total ezetimibe approximately 55%. The incremental LDL-C reduction due to adding ezetimibe to cholestyramine may be reduced by this interaction.

7.13 Coumarin Anticoagulants

If LYPQOZET is added to warfarin, a coumarin anticoagulant, the International Normalized Ratio (INR) should be appropriately monitored.

8 USE IN SPECIFIC POPULATIONS

8.1 Pregnancy

Pregnancy Category X.
[See Contraindications (4).]

Ezetimibe and Atorvastatin Tablets
Ezetimibe and atorvastatin tablets are contraindicated in women who are or may become pregnant. Serum cholesterol and triglycerides increase during normal pregnancy. Lipid-lowering drugs offer no benefit during pregnancy, because cholesterol and cholesterol derivatives are needed for normal fetal development. Atherosclerosis is a chronic process, and discontinuation of lipid-lowering drugs during pregnancy should have little impact on long-term outcomes of primary hypercholesterolemia therapy.

There are no adequate and well-controlled studies of ezetimibe and atorvastatin tablets use during pregnancy. There have been rare reports of congenital anomalies following intrauterine exposure to statins. In a review of about 100 prospectively followed pregnancies in women exposed to other statins, the incidences of congenital anomalies, spontaneous abortions, and fetal deaths/stillbirths did not exceed the rate expected in the general population. However, this study was only able to exclude a three-to-four-fold increased risk of congenital anomalies over background incidence. In 89% of these cases, drug treatment started before pregnancy and stopped during the first trimester when pregnancy was identified.

Statins may cause fetal harm when administered to a pregnant woman. Because ezetimibe and atorvastatin tablets contain atorvastatin, ezetimibe and atorvastatin tablets should be administered to women of childbearing potential only when such patients are highly unlikely to conceive and have been informed of the potential hazards. If the woman becomes pregnant while taking ezetimibe and atorvastatin tablets, it should be discontinued immediately and the patient advised again as to the potential hazards to the fetus and the lack of known clinical benefit with continued use during pregnancy.

Ezetimibe
In oral (gavage) embryo-fetal development studies of ezetimibe conducted in rats and rabbits during organogenesis, there was no evidence of embryolethal effects at the doses tested (250, 500, 1000 mg/kg/day). In rats, increased incidences of common fetal skeletal findings (extra pair of thoracic ribs, unossified cervical vertebral centra, shortened ribs) were observed at 1000 mg/kg/day (~10 times the human exposure at 10 mg daily based on AUC0-24hr for total ezetimibe). In rabbits treated with ezetimibe, an increased incidence of extra thoracic ribs was observed at 1000 mg/kg/day (150 times the human exposure at 10 mg daily based on AUC0-24hr for total ezetimibe). Ezetimibe crossed the placenta when pregnant rats and rabbits were given multiple oral doses.

Multiple-dose studies of ezetimibe given in combination with statins in rats and rabbits during organogenesis result in higher ezetimibe and statin exposures. Reproductive findings occur at lower doses in combination therapy compared to monotherapy.

Atorvastatin
Atorvastatin crosses the rat placenta and reaches a level in fetal liver equivalent to that of maternal plasma. Atorvastatin was not teratogenic in rats at doses up to 300 mg/kg/day or in rabbits at doses up to 100 mg/kg/day. These doses resulted in multiples of about 30 times (rat) or 20 times (rabbit) the human exposure based on surface area (mg/m^2).

In a study in rats given 20, 100, or 225 mg/kg/day, from gestation Day 7 through to lactation Day 21 (weaning), there was decreased pup survival at birth, neonate, weaning, and maturity in pups of mothers dosed with 225 mg/kg/day. Body weight was decreased on Days 4 and 21 in pups of mothers dosed at 100 mg/kg/day; pup body weight was decreased at birth and at Days 4, 21, and 91 at 225 mg/kg/day. Pup development was delayed (rotarod performance at 100 mg/kg/day and acoustic startle at 225 mg/kg/day; pinnae detachment and eye opening at 225 mg/kg/day). These doses correspond to 6 times (100 mg/kg) and 22 times (225 mg/kg) the human AUC at 80 mg/day. Rare reports of congenital anomalies have been received following intrauterine exposure to statin reductase inhibitors.

8.3 Nursing Mothers

In rat studies, exposure to total ezetimibe in nursing pups was up to half of that observed in maternal plasma. It is not known whether ezetimibe is excreted into human breast milk.

It is not known whether atorvastatin is excreted in human milk, but a small amount of another drug in this class does pass into breast milk. Nursing rat pups had plasma and liver atorvastatin levels of 50% and 40%, respectively, of that in their mother’s milk. Because of the potential for adverse reactions in nursing infants, women taking ezetimibe and atorvastatin tablets should not breastfeed [see Contraindications (4)].

8.4 Pediatric Use

Ezetimibe and Atorvastatin Tablets
Safety and effectiveness have not been established in pediatric patients.

Ezetimibe
Based on total ezetimibe (ezetimibe + ezetimibe-glucuronide) there are no pharmacokinetic differences between adolescents and adults. Pharmacokinetic data in the pediatric population <10 years of age are not available.

Atorvastatin
Pharmacokinetic data in the pediatric population are not available.

8.5 Geriatric Use

Of the patients who received ezetimibe coadministered with atorvastatin in clinical studies, 1166 were 65 and older (this included 291 who were 75 and older). The effectiveness and safety of ezetimibe and atorvastatin tablets were similar between these patients and younger subjects. Greater sensitivity of some older individuals cannot be ruled out. Since advanced age (≥65 years) is a predisposing factor for myopathy, ezetimibe and atorvastatin tablets should be prescribed with caution in the elderly [see Clinical Pharmacology (12.3)].

In geriatric patients, no dosage adjustment of ezetimibe and atorvastatin tablets is necessary.

8.6 Hepatic Impairment

Ezetimibe and atorvastatin tablets are contraindicated in patients with active liver disease or unexplained persistent elevations in hepatic transaminase levels [see Contraindications (4), Warnings and Precautions (5.3), and Clinical Pharmacology (12.3)].

8.7 Renal Impairment

A history of renal impairment may be a risk factor for statin-associated myopathy. These patients merit closer monitoring for skeletal muscle effects [see Warnings and Precautions (5.1)].

In patients with renal impairment, no dosage adjustment of ezetimibe and atorvastatin tablets is necessary.

10 OVERDOSAGE

LYPQOZET
No specific treatment of overdosage with LYPQOZET can be recommended. In the event of an overdose, the patient should be treated symptomatically, and supportive measures instituted as required.

Ezetimibe
In clinical studies, administration of ezetimibe, 50 mg/day to 15 healthy subjects for up to 14 days, 40 mg/day to 18 patients with primary hyperlipidemia for up to 56 days, and 40 mg/day to 27 patients with homozygous sitosterolemia for 26 weeks, was generally well tolerated. One female patient with homozygous sitosterolemia took an accidental overdose of ezetimibe 120 mg/day for 28 days with no reported clinical or laboratory adverse events.

Atorvastatin
Due to extensive drug binding to plasma proteins, hemodialysis is not expected to significantly enhance atorvastatin clearance.

11 DESCRIPTION

LYPQOZET contains ezetimibe, a selective inhibitor of intestinal cholesterol and related phytosterol absorption, and atorvastatin, a 3-hydroxy-3-methylglutaryl-coenzyme A (HMG-CoA) reductase inhibitor.

The chemical name of ezetimibe is 1-(4-fluorophenyl)-3(R)-[3-(4-fluorophenyl)-3(S)-hydroxypropyl]-4(S)-(4-hydroxyphenyl)-2-azetidinone. The molecular formula is C24H21F2NO3. Its molecular weight is 409.4.

Ezetimibe, USP is a white, crystalline powder that is freely to very soluble in ethanol, methanol, and acetone and practically insoluble in water. Its structural formula is:

Atorvastatin is [R-(R*, R*)]-2-(4-fluorophenyl)-ß, δ,-dihydroxy-5-(1-methylethyl)-3-phenyl-4-[(phenylamino) carbonyl]-1H-pyrrole-1-heptanoic acid, calcium salt (2:1).

Atorvastatin calcium, USP is a white to off-white amorphous powder that is very slightly soluble in water, insoluble in acetonitrile, and soluble in methanol. The molecular formula of atorvastatin calcium, USP is (C33H34FN2O5)2Ca. The molecular weight of atorvastatin calcium is 1155.37. Its structural formula is:

LYPQOZET is available for oral use as tablets containing 10 mg of ezetimibe and: 10.34 mg of atorvastatin calcium, equivalent to 10 mg of atorvastatin (LYPQOZET 10 mg/10 mg); 20.68 mg of atorvastatin calcium, equivalent to 20 mg of atorvastatin (LYPQOZET 10 mg/20 mg); 41.37 mg of atorvastatin calcium, equivalent to 40 mg of atorvastatin (LYPQOZET 10 mg/40 mg); or 82.73 mg of atorvastatin calcium, equivalent to 80 mg of atorvastatin (LYPQOZET 10 mg/80 mg). Each film-coated tablet of LYPQOZET contain the following inactive ingredients: calcium carbonate, colloidal silicon dioxide, croscarmellose sodium, hydroxypropyl cellulose, hypromellose, lactose monohydrate, magnesium stearate, microcrystalline cellulose, polyethylene glycol 8000, polysorbate 80, red 30 iron oxide, sodium lauryl sulfate, talc and titanium dioxide.

12 CLINICAL PHARMACOLOGY

12.1 Mechanism of Action

LYPQOZET
Plasma cholesterol is derived from intestinal absorption and endogenous synthesis. LYPQOZET contains ezetimibe and atorvastatin, two lipid-lowering compounds with complementary mechanisms of action.

Ezetimibe
Ezetimibe reduces blood cholesterol by inhibiting the absorption of cholesterol by the small intestine. The molecular target of ezetimibe has been shown to be the sterol transporter, Niemann-Pick C1-Like 1 (NPC1L1), which is involved in the intestinal uptake of cholesterol and phytosterols. In a 2-week clinical study in 18 hypercholesterolemic patients, ezetimibe inhibited intestinal cholesterol absorption by 54%, compared with placebo. Ezetimibe had no clinically meaningful effect on the plasma concentrations of the fat-soluble vitamins A, D, and E and did not impair adrenocortical steroid hormone production.

Ezetimibe does not inhibit cholesterol synthesis in the liver or increase bile acid excretion. Ezetimibe localizes at the brush border of the small intestine and inhibits the absorption of cholesterol, leading to a decrease in the delivery of intestinal cholesterol to the liver. This causes a reduction of hepatic cholesterol stores and an increase in clearance of cholesterol from the blood; this distinct mechanism is complementary to that of statins [see Clinical Studies (14)].

Atorvastatin
In animal models, atorvastatin lowers plasma cholesterol and lipoprotein levels by inhibiting HMG-CoA reductase and cholesterol synthesis in the liver and by increasing the number of hepatic LDL receptors on the cell-surface to enhance uptake and catabolism of LDL; atorvastatin also reduces LDL production and the number of LDL particles.

12.2 Pharmacodynamics

Clinical studies have demonstrated that elevated levels of total-C, LDL-C and Apo B, the major protein constituent of LDL, promote human atherosclerosis. In addition, decreased levels of HDL-C are associated with the development of atherosclerosis. Epidemiologic studies have established that cardiovascular morbidity and mortality vary directly with the level of total-C and LDL-C and inversely with the level of HDL-C. Like LDL, cholesterol-enriched triglyceride-rich lipoproteins, including very-low-density lipoproteins (VLDL), intermediate-density lipoproteins (IDL), and remnants, can also promote atherosclerosis. The independent effect of raising HDL-C or lowering TG on the risk of coronary and cardiovascular morbidity and mortality has not been determined.

Atorvastatin as well as some of its metabolites are pharmacologically active in humans. The liver is the primary site of action and the principal site of cholesterol synthesis and LDL clearance. Drug dosage, rather than systemic drug concentration, correlates better with LDL-C reduction. Individualization of drug dosage should be based on therapeutic response [see Dosage and Administration (2)].

12.3 Pharmacokinetics

LYPQOZET
LYPQOZET has been shown to be bioequivalent to coadministration of corresponding doses of ezetimibe and atorvastatin tablets.

Absorption
Ezetimibe
After oral administration, ezetimibe is absorbed and extensively conjugated to a pharmacologically active phenolic glucuronide (ezetimibe-glucuronide).

Atorvastatin
Maximum plasma atorvastatin concentrations after oral administration occur within 1 to 2 hours. Extent of absorption increases in proportion to atorvastatin dose. The absolute bioavailability of atorvastatin (parent drug) is approximately 14% and the systemic availability of HMG-CoA reductase inhibitory activity is approximately 30%. The low systemic availability is attributed to presystemic clearance in gastrointestinal mucosa and/or hepatic first-pass metabolism. Plasma atorvastatin concentrations are lower (approximately 30% for Cmax and AUC) following evening drug administration compared with morning. However, LDL-C reduction is the same regardless of the time of day of drug administration.

Effect of Food on Oral Absorption
LYPQOZET
When LYPQOZET 10/80 tablet was administered with a high-fat meal, atorvastatin Cmax decreased by 7% and no effect on atorvastatin AUC was observed. A high-fat meal had no effect on the pharmacokinetics of unconjugated ezetimibe.

LYPQOZET can be taken with or without food [see Dosage and Administration (2.1)].

Distribution
Ezetimibe
Ezetimibe and ezetimibe-glucuronide are highly bound (>90%) to human plasma proteins.

Atorvastatin
Mean volume of distribution of atorvastatin is approximately 381 liters. Atorvastatin is ≥98% bound to plasma proteins. A blood/plasma ratio of approximately 0.25 indicates poor drug penetration into red blood cells. Based on observations in rats, atorvastatin is likely to be secreted in human milk [see Contraindications (4); Use in Specific Populations (8.3)].

Metabolism and Excretion
Ezetimibe
Ezetimibe is primarily metabolized in the small intestine and liver via glucuronide conjugation with subsequent biliary and renal excretion. Minimal oxidative metabolism has been observed in all species evaluated.

In humans, ezetimibe is rapidly metabolized to ezetimibe-glucuronide. Ezetimibe and ezetimibe-glucuronide are the major drug-derived compounds detected in plasma, constituting approximately 10 to 20% and 80 to 90% of the total drug in plasma, respectively. Both ezetimibe and ezetimibe-glucuronide are eliminated from plasma with a half-life of approximately 22 hours for both ezetimibe and ezetimibe-glucuronide. Plasma concentration-time profiles exhibit multiple peaks, suggesting enterohepatic recycling.

Following oral administration of ^14C-ezetimibe (20 mg) to human subjects, total ezetimibe (ezetimibe + ezetimibe-glucuronide) accounted for approximately 93% of the total radioactivity in plasma. After 48 hours, there were no detectable levels of radioactivity in the plasma.

Approximately 78% and 11% of the administered radioactivity were recovered in the feces and urine, respectively, over a 10-day collection period. Ezetimibe was the major component in feces and accounted for 69% of the administered dose, while ezetimibe-glucuronide was the major component in urine and accounted for 9% of the administered dose.

Atorvastatin
Atorvastatin is extensively metabolized to ortho- and para hydroxylated derivatives and various beta-oxidation products. In vitro inhibition of HMG-CoA reductase by ortho- and para hydroxylated metabolites is equivalent to that of atorvastatin. Approximately 70% of circulating inhibitory activity for HMG-CoA reductase is attributed to active metabolites. In vitro studies suggest the importance of atorvastatin metabolism by cytochrome P450 3A4, consistent with increased plasma concentrations of atorvastatin in humans following coadministration with erythromycin, a known inhibitor of this isozyme [see Drug Interactions (7.1)]. In animals, the ortho-hydroxy metabolite undergoes further glucuronidation.

Atorvastatin and its metabolites are eliminated primarily in bile following hepatic and/or extra-hepatic metabolism; however, the drug does not appear to undergo enterohepatic recirculation. Mean plasma elimination half-life of atorvastatin in humans is approximately 14 hours, but the half-life of inhibitory activity for HMG-CoA reductase is 20 to 30 hours due to the contribution of active metabolites. Less than 2% of a dose of atorvastatin is recovered in urine following oral administration.

Specific Populations
Geriatric Patients
Ezetimibe
In a multiple-dose study with ezetimibe given 10 mg once daily for 10 days, plasma concentrations for total ezetimibe were about 2-fold higher in older (≥65 years) healthy subjects compared to younger subjects.

Atorvastatin
Plasma concentrations of atorvastatin are higher (approximately 40% for Cmax and 30% for AUC) in healthy elderly subjects (age ≥65 years) than in young adults. Clinical data suggest a greater degree of LDL-lowering at any dose of drug in the elderly patient population compared to younger adults.

Pediatric Patients:[See Use in Specific Populations (8.4).]
Gender
Ezetimibe
In a multiple-dose study with ezetimibe given 10 mg once daily for 10 days, plasma concentrations for total ezetimibe were slightly higher (<20%) in women than in men.

Atorvastatin
Plasma concentrations of atorvastatin in women differ from those in men (approximately 20% higher for Cmax and 10% lower for AUC); however, there is no clinically significant difference in LDL-C reduction with atorvastatin between men and women.

Race
Ezetimibe
Based on a meta-analysis of multiple-dose pharmacokinetic studies, there were no pharmacokinetic differences between Black and Caucasian subjects. Studies in Asian subjects indicated that the pharmacokinetics of ezetimibe were similar to those seen in Caucasian subjects.

Hepatic Impairment
Ezetimibe
After a single 10-mg dose of ezetimibe, the mean AUC for total ezetimibe was increased approximately 1.7-fold in patients with mild hepatic impairment (Child-Pugh score 5 to 6), compared to healthy subjects. The mean AUC values for total ezetimibe and ezetimibe increased approximately 3- to 4-fold and 5- to 6-fold, respectively, in patients with moderate (Child-Pugh score 7 to 9) or severe hepatic impairment (Child-Pugh score 10 to 15). In a 14-day, multiple-dose study (10 mg daily) in patients with moderate hepatic impairment, the mean AUC for total ezetimibe and ezetimibe increased approximately 4-fold on both Day 1 and Day 14 when compared to healthy subjects.

Atorvastatin
In patients with chronic alcoholic liver disease, plasma concentrations of atorvastatin are markedly increased. Cmax and AUC are each 4-fold greater in patients with Child-Pugh A disease. Cmax and AUC are approximately 16-fold and 11-fold increased, respectively, in patients with Child-Pugh B disease [see Contraindications (4)].

Renal Impairment
[See Warnings and Precautions (5.1), Use in Specific Populations (8.7)]

Ezetimibe
After a single 10-mg dose of ezetimibe in patients with severe renal disease (n=8; mean CrCl ≤30 mL/min/1.73 m^2), the mean AUC values for total ezetimibe, ezetimibe-glucuronide, and ezetimibe were increased approximately 1.5-fold, compared to healthy subjects (n=9).

Atorvastatin
Renal disease has no influence on the plasma concentrations or LDL-C reduction of atorvastatin.

Hemodialysis
Atorvastatin
While studies have not been conducted in patients with end-stage renal disease, hemodialysis is not expected to significantly enhance clearance of atorvastatin since the drug is extensively bound to plasma proteins.

Drug Interactions [See also Drug Interactions (7).]
No clinically significant pharmacokinetic interaction was seen when ezetimibe was coadministered with atorvastatin. Specific pharmacokinetic drug interaction studies with LYPQOZET have not been performed.

Cytochrome P450: Ezetimibe had no significant effect on a series of probe drugs (caffeine, dextromethorphan, tolbutamide, and IV midazolam) known to be metabolized by cytochrome P450 (1A2, 2D6, 2C8/9 and 3A4) in a "cocktail" study of twelve healthy adult males. This indicates that ezetimibe is neither an inhibitor nor an inducer of these cytochrome P450 isozymes, and it is unlikely that ezetimibe will affect the metabolism of drugs that are metabolized by these enzymes.

Atorvastatin is metabolized by cytochrome P450 3A4. Concomitant administration of LYPQOZET with inhibitors of cytochrome P450 3A4 can lead to increases in plasma concentrations of the atorvastatin component of LYPQOZET. The extent of interaction and potentiation of effects depends on the variability of effect on cytochrome P450 3A4.

Ezetimibe

Table 5: Effect of Coadministered Drugs on Total Ezetimibe
Coadministered Drug and Dosing Regimen | Total Ezetimibe*
Coadministered Drug and Dosing Regimen | Change in AUC | Change in Cmax
Cyclosporine-stable dose required (75 to 150 mg BID)†,‡ | ↑240% | ↑290%
Fenofibrate, 200 mg QD, 14 days‡ | ↑48% | ↑64%
Gemfibrozil, 600 mg BID, 7 days‡ | ↑64% | ↑91%
Cholestyramine, 4 g BID, 14 days‡ | ↓55% | ↓4%
Aluminum & magnesium hydroxide combination antacid, single dose§ | ↓4% | ↓30%
Cimetidine, 400 mg BID, 7 days | ↑6% | ↑22%
Glipizide, 10 mg, single dose | ↑4% | ↓8%
Statins
Lovastatin 20 mg QD, 7 days | ↑9% | ↑3%
Pravastatin 20 mg QD, 14 days | ↑7% | ↑23%
Atorvastatin 10 mg QD, 14 days | ↓2% | ↑12%
Rosuvastatin 10 mg QD, 14 days | ↑13% | ↑18%
Fluvastatin 20 mg QD, 14 days | ↓19% | ↑7%

* Based on 10-mg dose of ezetimibe
†Post-renal transplant patients with mild impaired or normal renal function. In a different study, a renal transplant patient with severe renal impairment (creatinine clearance of 13.2 mL/min/1.73 m^2) who was receiving multiple medications, including cyclosporine, demonstrated a 12-fold greater exposure to total ezetimibe compared to healthy subjects.
‡ See Drug Interactions (7)
§ Supralox®, 20 mL

Table 6: Effect of Ezetimibe Coadministration on Systemic Exposure to Other Drugs
Coadministered Drug and its Dosage Regimen | Ezetimibe Dosage Regimen | Change in AUC of Coadministered Drug | Change in Cmax of Coadministered Drug
Warfarin, 25 mg single dose on Day 7 | 10 mg QD, 11 days | ↓2% (R-warfarin) ↓4% (S-warfarin) | ↑3% (R-warfarin) ↑1% (S-warfarin)
Digoxin, 0.5 mg single dose | 10 mg QD, 8 days | ↑2% | ↓7%
Gemfibrozil, 600 mg BID, 7 days* | 10 mg QD, 7 days | ↓1% | ↓11%
Ethinyl estradiol & Levonorgestrel, QD, 21 days | 10 mg QD, Days 8 to14 of 21 d oral contraceptive cycle | Ethinyl estradiol 0% Levonorgestrel 0% | Ethinyl estradiol ↓9% Levonorgestrel ↓5%
Glipizide, 10 mg on Days 1 and 9 | 10 mg QD, Days 2 to 9 | ↓3% | ↓5%
Fenofibrate, 200 mg QD, 14 days* | 10 mg QD, 14 days | ↑11% | ↑7%
Cyclosporine, 100 mg single dose Day 7* | 20 mg QD, 8 days | ↑15% | ↑10%
Statins
Lovastatin 20 mg QD, 7 days | 10 mg QD, 7 days | ↑19% | ↑3%
Pravastatin 20 mg QD, 14 days | 10 mg QD, 14 days | ↓20% | ↓24%
Atorvastatin 10 mg QD, 14 days | 10 mg QD, 14 days | ↓4% | ↑7%
Rosuvastatin 10 mg QD, 14 days | 10 mg QD, 14 days | ↑19% | ↑17%
Fluvastatin 20 mg QD, 14 days | 10 mg QD, 14 days | ↓39% | ↓27%

* See Drug Interactions (7)

Atorvastatin

Table 7: Effect of Coadministered Drugs on the Pharmacokinetics of Atorvastatin
Coadministered Drug and Dosing Regimen | Atorvastatin
 | Dose (mg) | Change in AUC* | Change in Cmax *
Cyclosporine 5.2 mg/kg/day, stable dose† | 10 mg QD for 28 days | ↑8.7 fold | ↑10.7 fold
Tipranavir 500 mg BID/ritonavir 200 mg BID, 7 days† | 10 mg, SD | ↑9.4 fold | ↑8.6 fold
Telaprevir 750 mg q8h, 10 days† | 20 mg, SD | ↑7.88 fold | ↑10.6 fold
Saquinavir 400 mg BID/ritonavir 400 mg BID, 15 days†,# | 40 mg QD for 4 days | ↑3.9 fold | ↑4.3 fold
Clarithromycin 500 mg BID, 9 days† | 80 mg QD for 8 days | ↑4.4 fold | ↑5.4 fold
Darunavir 300 mg BID/ritonavir 100 mg BID, 9 days† | 10 mg QD for 4 days | ↑3.4 fold | ↑2.25 fold
Itraconazole 200 mg QD, 4 days† | 40 mg, SD | ↑3.3 fold | ↑20%
Fosamprenavir 700 mg BID/ritonavir 100 mg BID, 14 days† | 10 mg QD for 4 days | ↑2.53 fold | ↑2.84 fold
Fosamprenavir 1400 mg BID, 14 days† | 10 mg QD for 4 days | ↑2.3 fold | ↑4.04 fold
Nelfinavir 1250 mg BID, 14 days† | 10 mg QD for 28 days | ↑74% | ↑2.2 fold
Grapefruit Juice, 240 mL QD†,‡ | 40 mg, SD | ↑37% | ↑16%
Diltiazem 240 mg QD, 28 days | 40 mg, SD | ↑51% | No change
Erythromycin 500 mg QID, 7 days | 10 mg, SD | ↑33% | ↑38%
Amlodipine 10 mg, single dose | 80 mg, SD | ↑15% | ↓12%
Cimetidine 300 mg QD, 4 weeks | 10 mg QD for 2 weeks | ↓Less than 1% | ↓11%
Colestipol 10 mg BID, 28 weeks | 40 mg QD for 28 weeks | Not determined | ↓26%§
Maalox TC® 30 mL QD, 17 days | 10 mg QD for 15 days | ↓33% | ↓34%
Efavirenz 600 mg QD, 14 days | 10 mg for 3 days | ↓41% | ↓1%
Rifampin 600 mg QD, 7 days (coadministered) †,¶ | 40 mg, SD | ↑30% | ↑2.7 fold
Rifampin 600 mg QD, 5 days (doses separated) †,¶ | 40 mg, SD | ↓80% | ↓40%
Gemfibrozil 600 mg BID, 7 days† | 40 mg, SD | ↑35% | ↓Less than 1%
Fenofibrate 160 mg QD, 7 days† | 40 mg, SD | ↑3% | ↑2%
Boceprevir 800 mg TID, 7 days | 40 mg, SD | ↑2.30 fold | ↑2.66 fold
Grazoprevir 200 mg + Elbasvir 50 mg QD, 13 days | 10 mg, SD | ↑1.9 fold | ↑4.34 fold

* Data given as x-fold change represent a simple ratio between coadministration and atorvastatin alone (i.e., 1-fold = no change). Data given as % change represent % difference relative to atorvastatin alone (i.e., 0% = no change).
† See Warnings and Precautions (5.1) and Drug Interactions (7) for clinical significance.
‡ Greater increases in AUC (up to 2.5 fold) and/or Cmax (up to 71%) have been reported with excessive grapefruit consumption (≥750 mL to 1.2 liters per day).
§ Single sample taken 8 to16 h post-dose.
¶ Due to the dual interaction mechanism of rifampin, simultaneous coadministration of atorvastatin with rifampin is recommended, as delayed administration of atorvastatin after administration of rifampin has been associated with a significant reduction in atorvastatin plasma concentrations.
# The dose of saquinavir plus ritonavir in this study is not the clinically used dose. The increase in atorvastatin exposure when used clinically is likely to be higher than what was observed in this study. Therefore, caution should be applied and the lowest dose necessary should be used.

Table 8: Effect of Atorvastatin on the Pharmacokinetics of Coadministered Drugs
Atorvastatin | Coadministered Drug and Dosing Regimen
 | Drug/Dose (mg) | Change in AUC | Change in Cmax
80 mg QD for 15 days | Antipyrine, 600 mg SD | ↑3% | ↓11%
80 mg QD for 14 days | Digoxin 0.25 mg QD, 20 days* | ↑15% | ↑20%
40 mg QD for 22 days | Oral contraceptive QD, 2 months; - norethindrone 1 mg - ethinyl estradiol 35 mcg | ↑28% ↑19% | ↑23% ↑30%
10 mg, SD | Tipranavir 500 mg BID/ritonavir 200 mg BID, 7 days | No change | No change
10 mg QD for 4 days | Fosamprenavir 1400 mg BID, 14 days | ↓27% | ↓18%
10 mg QD for 4 days | Fosamprenavir 700 mg BID/ritonavir 100 mg BID, 14 days | No change | No change

* See Drug Interactions (7) for clinical significance.

13 NONCLINICAL TOXICOLOGY

13.1 Carcinogenesis, Mutagenesis, Impairment of Fertility

No animal carcinogenicity or fertility studies have been conducted with the combination of ezetimibe and atorvastatin. The combination of ezetimibe with atorvastatin did not show evidence of mutagenicity in vitro in a microbial mutagenicity (Ames) test with Salmonella typhimurium and Escherichia coli with or without metabolic activation. No evidence of clastogenicity was observed in vitro in a chromosomal aberration assay in human peripheral blood lymphocytes with ezetimibe and atorvastatin with or without metabolic activation. There was no evidence of genotoxicity at doses up to 250 mg/kg with the combination of ezetimibe and atorvastatin (1:1) in the in vivo mouse micronucleus test.

Ezetimibe
A 104-week dietary carcinogenicity study with ezetimibe was conducted in rats at doses up to 1500 mg/kg/day (males) and 500 mg/kg/day (females) (~20 times the human exposure at 10 mg daily based on AUC0-24hr for total ezetimibe). A 104-week dietary carcinogenicity study with ezetimibe was also conducted in mice at doses up to 500 mg/kg/day (>150 times the human exposure at 10 mg daily based on AUC0-24hr for total ezetimibe). There were no statistically significant increases in tumor incidences in drug-treated rats or mice.

No evidence of mutagenicity was observed in vitro in a microbial mutagenicity (Ames) test with Salmonella typhimurium and Escherichia coli with or without metabolic activation. No evidence of clastogenicity was observed in vitro in a chromosomal aberration assay in human peripheral blood lymphocytes with or without metabolic activation. In addition, there was no evidence of genotoxicity in the in vivo mouse micronucleus test.

In oral (gavage) fertility studies of ezetimibe conducted in rats, there was no evidence of reproductive toxicity at doses up to 1000 mg/kg/day in male or female rats (~7 times the human exposure at 10 mg daily based on AUC0-24hr for total ezetimibe).

Atorvastatin
In a 2-year carcinogenicity study in rats at dose levels of 10, 30, and 100 mg/kg/day, 2 rare tumors were found in muscle in high-dose females: in one, there was a rhabdomyosarcoma and, in another, there was a fibrosarcoma. This dose represents a plasma AUC0-24hr value of approximately 16 times the mean human plasma drug exposure after an 80-mg oral dose.

A 2-year carcinogenicity study in mice given 100, 200, or 400 mg/kg/day resulted in a significant increase in liver adenomas in high-dose males and liver carcinomas in high-dose females. These findings occurred at plasma AUC0-24hr values of approximately 6 times the mean human plasma drug exposure after an 80-mg oral dose.

In vitro, atorvastatin was not mutagenic or clastogenic in the following tests with and without metabolic activation: the Ames test with Salmonella typhimurium and Escherichia coli, the HGPRT forward mutation assay in Chinese hamster lung cells, and the chromosomal aberration assay in Chinese hamster lung cells. Atorvastatin was negative in the in vivo mouse micronucleus test.

Studies in rats performed at doses up to 175 mg/kg (15 times the human exposure) produced no changes in fertility. There was aplasia and aspermia in the epididymis of 2 of 10 rats treated with 100 mg/kg/day of atorvastatin for 3 months (16 times the human AUC at the 80-mg dose); testis weights were significantly lower at 30 and 100 mg/kg and epididymal weight was lower at 100 mg/kg. Male rats given 100 mg/kg/day for 11 weeks prior to mating had decreased sperm motility, spermatid head concentration, and increased abnormal sperm. Atorvastatin caused no adverse effects on semen parameters, or reproductive organ histopathology in dogs given doses of 10, 40, or 120 mg/kg for two years.

13.2 Animal Toxicology and/or Pharmacology

Ezetimibe
In a rat model, where the glucuronide metabolite of ezetimibe (ezetimibe-glucuronide) was administered intraduodenally, the metabolite was as potent as ezetimibe in inhibiting the absorption of cholesterol, suggesting that the glucuronide metabolite had activity similar to the parent drug.

In 1-month studies in dogs given ezetimibe (0.03 to 300 mg/kg/day), the concentration of cholesterol in gallbladder bile increased ~2- to 4-fold. However, a dose of 300 mg/kg/day administered to dogs for one year did not result in gallstone formation or any other adverse hepatobiliary effects. In a 14-day study in mice given ezetimibe (0.3 to 5 mg/kg/day) and fed a low-fat or cholesterol-rich diet, the concentration of cholesterol in gallbladder bile was either unaffected or reduced to normal levels, respectively.

A series of acute preclinical studies was performed to determine the selectivity of ezetimibe for inhibiting cholesterol absorption. Ezetimibe inhibited the absorption of ^14C-cholesterol with no effect on the absorption of triglycerides, fatty acids, bile acids, progesterone, ethinyl estradiol, or the fat-soluble vitamins A and D.

In 4- to 12-week toxicity studies in mice, ezetimibe did not induce cytochrome P450 drug metabolizing enzymes. In toxicity studies, a pharmacokinetic interaction of ezetimibe with statins (parents or their active hydroxy acid metabolites) was seen in rats, dogs, and rabbits.

14 CLINICAL STUDIES

14.1 Primary Hyperlipidemia

Ezetimibe and Atorvastatin Tablets - Lipid Efficacy
Ezetimibe and atorvastatin tablets reduce total-C, LDL-C, Apo B, TG, and non-HDL-C, and increases HDL-C in patients with hypercholesterolemia.

Ezetimibe and atorvastatin tablets are effective in men and women with hyperlipidemia. Experience in non-Caucasians is limited and does not permit a precise estimate of the magnitude of the effects of ezetimibe and atorvastatin tablets.

In a multicenter, double-blind, placebo-controlled, clinical study in patients with hyperlipidemia, 628 patients were treated for up to 12 weeks and 246 for up to an additional 48 weeks. Patients were randomized to receive placebo, ezetimibe (10 mg), atorvastatin (10 mg, 20 mg, 40 mg, or 80 mg), or coadministered ezetimibe and atorvastatin equivalent to ezetimibe and atorvastatin tablets (10/10, 10/20, 10/40, and 10/80) in the 12-week study. After completing the 12-week study, patients who agreed to participate in the study extension were assigned to coadministered ezetimibe and atorvastatin equivalent to ezetimibe and atorvastatin tablets (10/10 to 10/80) or atorvastatin (10 to 80 mg/day) for an additional 48 weeks.

The patient population was: 59% female; 85% Caucasian, 6% Black, 3% Asian, 5% Hispanic, 1% American Indian, <1% other; 18 to 86 years of age (mean age 57 years).

Patients receiving all doses of ezetimibe and atorvastatin tablets were compared to those receiving all doses of atorvastatin. Ezetimibe and atorvastatin tablets lowered total-C, LDL-C, Apo B, TG, and non-HDL-C, and increased HDL-C significantly more than atorvastatin alone. (See Table 9.)

Table 9: Response to Ezetimibe and Atorvastatin Tablets in Patients with Primary Hyperlipidemia (Mean* % Change from Untreated Baseline† at 12 weeks)
Treatment; (Daily Dose) | N | Total-C; [Baseline§] | LDL-C; [Baseline§] | Apo B; [Baseline§] | TG*; [Baseline§] | HDL-C; [Baseline§] | Non-HDL-C; [Baseline§]
Pooled data (All ezetimibe and atorvastatin tablets doses)‡ | 255 | -41% [267] | -56% [182] | -45% [170] | -33% [165] | +7% [50.8] | -52% [217]
Pooled data (All atorvastatin doses)‡ | 248 | -32% [269] | -44% [181] | -36% [168] | -24% [155] | +4% [53.7] | -41% [215]
Ezetimibe 10 mg | 65 | -14% [259] | -20% [177] | -15% [167] | -5% [145] | +4% [50.6] | -18% [209]
Placebo | 60 | +4% [262] | +4% [180] | +3% [168] | -6% [143] | +4% [50.4] | +4% [212]
Ezetimibe and atorvastatin tablets by dose
10/10 | 65 | -38% [262] | -53% [177] | -43% [165] | -31% [158] | +9% [51.9] | -49% [211]
10/20 | 62 | -39% [269] | -54% [184] | -44% [174] | -30% [165] | +9% [49.3] | -50% [220]
10/40 | 65 | -42% [271] | -56% [184] | -45% [173] | -34% [180] | +5% [51.1] | -52% [220]
10/80 | 63 | -46% [267] | -61% [183] | -50% [169] | -40% [146] | +7% [50.9] | -58% [216]
Atorvastatin by dose
10 mg | 60 | -26% [271] | -37% [185] | -28% [168] | -21% [153] | +6% [53.7] | -34% [217]
20 mg | 60 | -30% [267] | -42% [177] | -34% [164] | -23% [147] | +4% [55.5] | -39% [211]
40 mg | 66 | -32% [266] | -45% [180] | -37% [167] | -24% [159] | +4% [53.0] | -41% [213]
80 mg | 62 | -40% [270] | -54% [184] | -46% [171] | -31% [163] | +3% [52.7] | -51% [218]

* For triglycerides, median % change from baseline
†Baseline - on no lipid-lowering drug
‡Ezetimibe and atorvastatin tablets pooled (10/10 to 10/80) significantly reduced total-C, LDL-C, Apo B, TG, non-HDL-C, and significantly increased HDL-C compared to all doses of atorvastatin pooled (10 to 80 mg).
§ Baseline units: mg/dL; medians for TG, means for all other values

The changes in lipid endpoints after an additional 48 weeks of treatment with ezetimibe and atorvastatin tablets (all doses) or with atorvastatin (all doses) were generally consistent with the 12-week data displayed above in the 245 subjects (out of the 576 who completed the 12-week study) who agreed to participate in the study extension.

A multicenter, double-blind, controlled, 14-week study was conducted in 621 patients with heterozygous familial hypercholesterolemia (HeFH), coronary heart disease (CHD), or multiple cardiovascular risk factors (≥2), adhering to an NCEP Step I or stricter diet. All patients received atorvastatin 10 mg for a minimum of 4 weeks prior to randomization. Patients were then randomized to receive either coadministered ezetimibe and atorvastatin (equivalent to ezetimibe and atorvastatin tablets 10/10) or atorvastatin 20 mg/day monotherapy. Patients who did not achieve their LDL-C target goal after 4 and/or 9 weeks of randomized treatment were titrated to double the atorvastatin dose.

The patient population was: 47% female; 91% Caucasian, 2% Black, 2% Asian, 5% Hispanic, <1% other; 18 to 82 years of age (mean age 61 years).

Ezetimibe and atorvastatin tablets 10/10 was significantly more effective than doubling the dose of atorvastatin to 20 mg in further reducing total-C, LDL-C, TG, and non-HDL-C. Results for HDL-C between the two treatment groups were not significantly different. (See Table 10.) In addition, at Week 4 significantly more patients receiving ezetimibe and atorvastatin tablets 10/10 attained LDL-C <100 mg/dL (<2.6 mmol/L) compared to those receiving atorvastatin 20 mg, 12% vs. 2%. The baseline mean LDL-C levels for patients receiving ezetimibe and atorvastatin tablets 10/10 and atorvastatin 20 mg were 186 mg/dL and 187 mg/dL, respectively.

Table 10: Response to Ezetimibe and Atorvastatin Tablets after 4 Weeks in Patients with CHD or Multiple Cardiovascular Risk Factors and an LDL-C ≥130 mg/dL (Mean* % Change from Baseline†)
Treatment; (Daily Dose) | N | Total-C; [Baseline‡] | LDL-C; [Baseline‡] | HDL-C; [Baseline‡] | TG*; [Baseline‡] | Non-HDL-C; [Baseline‡]
Ezetimibe and atorvastatin tablets 10/10 | 305 | -17%§ [262] | -24%§ [186] | +2% [50.0] | -9%§ [117] | -22%§ [212]
Atorvastatin 20 mg | 316 | -6% [264] | -9% [187] | +1% [49.9] | -4% [119] | -8% [214]

* For triglycerides, median % change from baseline
†Patients on atorvastatin 10 mg, then switched to ezetimibe and atorvastatin tablets 10/10 or titrated to atorvastatin 20 mg
‡Baseline units: mg/dL; medians for TG, means for all other values
§ p<0.05 for difference with atorvastatin

The Titration of Atorvastatin Versus Ezetimibe Add-On to Atorvastatin in Patients with Hypercholesterolemia (TEMPO) study, a multicenter, double-blind, controlled, 6-week study, included 184 patients with an LDL-C level ≥100 mg/dL and ≤160 mg/dL (≥2.6 mmol/L and ≤4.1 mmol/L) and at moderate high risk for coronary heart disease (CHD). All patients received atorvastatin 20 mg for a minimum of 4 weeks prior to randomization. Patients not at the optional NCEP ATP III LDL-C level (<100 mg/dL [<2.6 mmol/L]) were randomized to receive either coadministered ezetimibe and atorvastatin (equivalent to ezetimibe and atorvastatin tablets 10/20) or atorvastatin 40 mg for 6 weeks.

The patient population was: 45% female; 60% Caucasian, 26% Multi-racial, 6% Black, 8% Asian, <1% American Indian or Alaska native; 24 to 78 years of age (mean age 58 years).

Ezetimibe and atorvastatin tablets 10/20 was significantly more effective than doubling the dose of atorvastatin to 40 mg in further reducing total-C, LDL-C, Apo B and non-HDL-C. Results for HDL-C and TG between the two treatment groups were not significantly different. (See Table 11.) In addition, significantly more patients receiving ezetimibe and atorvastatin tablets 10/20 attained LDL-C <100 mg/dL (<2.6 mmol/L) compared to those receiving atorvastatin 40 mg, 84% vs. 49%.

Table 11: Response to Ezetimibe and Atorvastatin Tablets in Patients with Primary Hypercholesterolemia (Mean* % Change from Baseline†)
Treatment; (Daily Dose) | N | Total-C; [Baseline‡] | LDL-C; [Baseline‡] | Apo B; [Baseline‡] | HDL-C; [Baseline‡] | TG*; [Baseline‡] | Non-HDL-C; [Baseline‡]
Ezetimibe and atorvastatin tablets 10/20 | 92 | -20%§ [203] | -31%§ [120] | -21%§ [123] | +3% [50.9] | -18% [155] | -27%§ [152]
Atorvastatin 40 mg | 92 | -7% [201] | -11% [118] | -8% [120] | +1% [52.1] | -6% [148] | -10% [149]

* For triglycerides, median % change from baseline
†Patients on atorvastatin 20 mg, then switched to ezetimibe and atorvastatin tablets 10/20 or titrated to atorvastatin 40 mg
‡Baseline units: mg/dL; medians for TG, means for all other values
§ p<0.05 for difference with atorvastatin

The Ezetimibe Plus Atorvastatin Versus Atorvastatin Titration in Achieving Lower LDL-C Targets in Hypercholesterolemic Patients (EZ-PATH) study, a multicenter, double-blind, controlled, 6-week study, included 556 patients with an LDL-C level ≥70 mg/dL and ≤160 mg/dL (≥1.8 mmol/L and ≤4.1 mmol/L) and at high risk for coronary heart disease (CHD). All patients received atorvastatin 40 mg for a minimum of 4 weeks prior to randomization. Patients not at the optional NCEP ATP III LDL-C level <70 mg/dL (<1.8 mmol/L) were randomized to receive either coadministered ezetimibe and atorvastatin (equivalent to ezetimibe and atorvastatin tablets 10/40) or atorvastatin 80 mg for 6 weeks.

The patient population was: 39% female; 81% Caucasian, 11% Black, 6% Multi-racial, 2% Asian; 31 to 80 years of age (mean age 52 years).

Ezetimibe and atorvastatin tablets 10/40 was significantly more effective than doubling the dose of atorvastatin to 80 mg in further reducing total-C, LDL-C, Apo B, TG, and non-HDL-C. Results for HDL-C between the two treatment groups were not significantly different. (See Table 12.) In addition, significantly more patients receiving ezetimibe and atorvastatin tablets 10/40 attained LDL-C <70 mg/dL (<1.8 mmol/L) compared to those receiving atorvastatin 80 mg, 74% vs. 32%.

Table 12: Response to Ezetimibe and Atorvastatin Tablets in Patients with Primary Hypercholesterolemia (Mean* % Change from Baseline†)
Treatment; (Daily Dose) | N | Total-C; [Baseline‡] | LDL-C; [Baseline‡] | Apo B; [Baseline‡] | HDL-C; [Baseline‡] | TG*; [Baseline‡] | Non-HDL-C; [Baseline‡]
Ezetimibe and atorvastatin tablets 10/40 | 277 | -17%§ [165] | -27%§ [89] | -18%§ [101] | 0% [47.7] | -12%§ [131] | -23%§ [117]
Atorvastatin 80 mg | 279 | -7% [165] | -11% [90] | -8% [102] | -1% [46.9] | -6% [136] | -9% [118]

* For triglycerides, median % change from baseline
† Patients on atorvastatin 20 mg, then switched to ezetimibe and atorvastatin tablets 10/40 or titrated to atorvastatin 80 mg
‡ Baseline units: mg/dL; medians for TG, means for all other values
§ p<0.05 for difference with atorvastatin

14.2 Homozygous Familial Hypercholesterolemia (HoFH)

A double-blind, randomized, 12-week study was performed in patients with a clinical and/or genotypic diagnosis of HoFH. Data were analyzed from a subgroup of patients (n=36) receiving atorvastatin 40 mg at baseline. Increasing the dose of atorvastatin from 40 to 80 mg (n=12) produced a reduction of LDL-C of 2% from baseline on atorvastatin 40 mg. Coadministered ezetimibe and atorvastatin equivalent to ezetimibe and atorvastatin tablets (10/40 and 10/80 pooled, n=24), produced a reduction of LDL-C of 19% from baseline on atorvastatin 40 mg. In those patients coadministered ezetimibe and atorvastatin equivalent to ezetimibe and atorvastatin tablets (10/80, n=12), a reduction of LDL-C of 25% from baseline on atorvastatin 40 mg was produced.

After completing the 12-week study, eligible patients (n=35), who were receiving atorvastatin 40 mg at baseline, were assigned to coadministered ezetimibe and atorvastatin equivalent to ezetimibe and atorvastatin tablets 10/40 for up to an additional 24 months. Following at least 4 weeks of treatment, the atorvastatin dose could be doubled to a maximum dose of 80 mg.

At the end of the 24 months, ezetimibe and atorvastatin tablets (10/40 and 10/80 pooled) produced a reduction of LDL-C that was consistent with that seen in the 12-week study.

16 HOW SUPPLIED/STORAGE AND HANDLING

LYPQOZET is available as follows:
10 mg/10 mg - White to off white, oval shaped film-coated tablets, debossed with “W 10” on one side and plain on other side containing 10 mg of ezetimibe, USP and 10.34 mg of atorvastatin calcium, USP, equivalent to 10 mg of atorvastatin.

Bottles of 30 ……………………………….70661-005-30
Bottles of 90 ……………………………….70661-005-90

10 mg/20 mg - White to off white, oval shaped film-coated tablets, debossed with “W 20” on one side and plain on other side containing 10 mg of ezetimibe, USP and 20.68 mg of atorvastatin calcium, USP, equivalent to 20 mg of atorvastatin.
Bottles of 30 ……………………………….70661-006-30
Bottles of 90 ……………………………….70661-006-90

10 mg/40 mg – White to off white, oval shaped film-coated tablets, debossed with “W 40” on one side and plain on other side containing 10 mg of ezetimibe, USP and 41.37 mg of atorvastatin calcium, USP, equivalent to 40 mg of atorvastatin.

Bottles of 30 ……………………………….70661-007-30
Bottles of 90 ……………………………….70661-007-90

10 mg/80 mg – White to off white, oval shaped film-coated tablets, debossed with “W 80” on one side and plain on other side containing 10 mg of ezetimibe, USP and 82.73 mg of atorvastatin calcium, USP, equivalent to 80 mg of atorvastatin.

Bottles of 30 ……………………………….70661-008-30
Bottles of 90 ……………………………….70661-008-90

Dispense in a tight, light-resistant container as defined in the USP.

Store at 20° to 25°C (68° to 77°F); excursions permitted to 15° to 30°C (between 59° to 86°F) [See USP Controlled Room Temperature]. Protect from moisture and light.

17 PATIENT COUNSELING INFORMATION

Advise the patient to read the FDA-Approved Patient Labeling (Patient Information).

Patients should be advised to adhere to their National Cholesterol Education Program (NCEP)-recommended diet, a regular exercise program, and periodic testing of a fasting lipid panel.

17.1 Muscle Pain

All patients starting therapy with LYPQOZET should be advised of the risk of myopathy and told to report promptly any unexplained muscle pain, tenderness or weakness particularly if accompanied by malaise or fever or if these muscle signs or symptoms persist after discontinuing LYPQOZET. The risk of this occurring is increased when taking certain types of medication or consuming larger quantities (>1 liter) of grapefruit juice. Patients should discuss all medication, both prescription and over-the-counter, with their physician.

17.2 Liver Enzymes

It is recommended that liver enzyme tests be performed before the initiation of LYPQOZET and if signs or symptoms of liver injury occur. All patients treated with LYPQOZET should be advised to report promptly any symptoms that may indicate liver injury, including fatigue, anorexia, right upper abdominal discomfort, dark urine, or jaundice.

17.3 Pregnancy

Women of childbearing age should be advised to use an effective method of birth control to prevent pregnancy while using LYPQOZET. Discuss future pregnancy plans with your patients, and discuss when to stop taking LYPQOZET if they are trying to conceive. Patients should be advised that if they become pregnant they should stop taking LYPQOZET and call their healthcare professional.

17.4 Breastfeeding

Women who are breastfeeding should be advised to not use LYPQOZET. Patients who have a lipid disorder and are breastfeeding should be advised to discuss the options with their healthcare professionals.

17.5 Important Storage and Administration Instructions

Patients should be advised to see the FDA-Approved Patient Labeling (Patient Information).

Tablets should be swallowed whole. Do not crush, dissolve, or chew tablets.

If a dose is missed, the patient should not take an extra dose. Just resume the usual schedule.

Brands listed are the trademarks of their respective owners.

Manufacturer for:
Althera Pharmaceuticals, LLC.,
1201 N Orange St, Suite 712,
Wilmington, DE 19801

Distributed by:
Althera Pharmaceuticals, LLC.,
Wilmington, DE 19801 USA

Revised: January 2024

PATIENT INFORMATION LYPQOZET® (LIP-ko-zett) (ezetimibe and atorvastatin) tablets

Rx Only

Read this information carefully before you start taking LYPQOZET and each time you get more LYPQOZET. There may be new information. This information does not take the place of talking with your doctor about your medical condition or your treatment. If you have any questions about LYPQOZET, ask your doctor. Only your doctor can determine if LYPQOZET is right for you.

What is LYPQOZET?
LYPQOZET contains 2 cholesterol-lowering medications, ezetimibe and atorvastatin.

LYPQOZET is a prescription medicine used to lower levels of total cholesterol, LDL (bad) cholesterol and fatty substances called triglycerides in the blood. In addition, LYPQOZET raise levels of HDL (good) cholesterol. LYPQOZET is for patients who cannot control their cholesterol levels by diet and exercise alone. You should stay on a cholesterol-lowering diet while taking this medicine.

LYPQOZET has not been shown to reduce heart attacks or strokes more than atorvastatin alone.

It is not known if LYPQOZET is safe and effective in children.

Who should not take LYPQOZET?

Do not take LYPQOZET if you:

- have active liver problems or repeated blood tests showing possible liver problems.
- are allergic to ezetimibe or atorvastatin or any of the ingredients in LYPQOZET. See the end of this leaflet for a complete list of ingredients in LYPQOZET.
- are pregnant or plan to become pregnant. LYPQOZET may harm your unborn baby. If you are a woman of childbearing age, you should use an effective method of birth control while taking LYPQOZET. Stop taking LYPQOZET and call your doctor right away if you get pregnant while taking LYPQOZET.
- are breastfeeding or plan to breastfeed. LYPQOZET can pass into your breast milk and may harm your baby. Talk to your doctor about the best way to feed your baby if you take LYPQOZET. Do not breastfeed while taking LYPQOZET.

What should I tell my doctor before taking LYPQOZET?

Before you take LYPQOZET, tell your doctor if you:

- have a thyroid problem
- have kidney problems
- have diabetes
- have unexplained muscle aches or weakness
- drink more than 2 glasses of alcohol daily or have or have had liver problems
- have any other medical conditions

Tell your doctor about all the medicines you take, including prescription and non-prescription medicines, vitamins, and herbal supplements.

Taking LYPQOZET with certain other medicines or substances can increase the risk of muscle problems or other side effects.

Especially tell your doctor if you take medicines for:

- your immune system
- cholesterol
- infections
- birth control
- heart failure
- HIV or AIDS
- hepatitis C
- gout

Also tell your doctor if you drink large amounts of grapefruit juice.

How should I take LYPQOZET?

- Take LYPQOZET exactly as your doctor tells you to take it.
- Your doctor will tell you how much LYPQOZET to take and when to take it.
- Your doctor may change your dose if needed.
- Do not open your LYPQOZET bottle until you are ready to take LYPQOZET.
- Take LYPQOZET 1 time each day, with or without food. It may be easier to remember to take your dose if you do it at the same time every day, such as with breakfast, dinner, or at bedtime.
- Tablets should be swallowed whole. Do not crush, dissolve, or chew tablets.
- Keep taking LYPQOZET unless your doctor tells you to stop. If you stop LYPQOZET your cholesterol may rise again.
- If you miss a dose, do not take an extra dose. Just resume your usual schedule.
- If you take too much LYPQOZET , call your doctor or Poison Control Center at 1-800-222-1222 or go to the nearest hospital emergency room right away.
- See your doctor regularly to check your cholesterol level and to check for side effects. Your doctor may do blood tests to check your liver before you start taking LYPQOZET and during treatment.

What should I avoid while taking LYPQOZET?

- Do not start any new medicines before talking to your doctor. This includes prescription and non-prescription medicines, vitamins, and herbal supplements. LYPQOZET and certain other medicines can interact causing serious side effects.
- Do not drink more than 2 glasses of alcohol daily.
- Do not get pregnant. If you get pregnant, stop taking LYPQOZET right away and call your doctor.

What are the possible side effects of LYPQOZET?

LYPQOZET may cause serious side effects, including:

- muscle problems. LYPQOZET can cause serious muscle problems that can lead to kidney problems, including kidney failure. You have a higher chance for muscle problems if you are taking certain other medicines with LYPQOZET.

Tell your doctor right away if:
o you have unexplained muscle pain, tenderness, or weakness, especially if you have a fever or feel more tired than usual, while you take LYPQOZET.
o you have muscle problems that do not go away even after your doctor has advised you to stop taking LYPQOZET. Your doctor may do further tests to diagnose the cause of your muscle problems.

• liver problems. Your doctor should do blood tests to check your liver before you start taking LYPQOZET and if you have symptoms of liver problems while you take LYPQOZET. Call your doctor right away if you have the following symptoms of liver problems:
o feel tired or weak
o loss of appetite
o upper belly pain
o dark urine
o yellowing of your skin or the whites of your eyes

Also call your doctor right away if you have:

- allergic reactions including swelling of the face, lips, tongue, and/or throat that may cause difficulty in breathing or swallowing which may require treatment right away
- nausea and vomiting
- passing brown or dark-colored urine
- you feel more tired than usual
- stomach pain
- allergic skin reactions

The most common side effects of LYPQOZET include:

- muscle and body pain
- changes in your liver function tests

Additional side effects that have been reported in people taking LYPQOZET, ezetimibe or atorvastatin in clinical studies or general use include: joint pain; diarrhea; tendon problems; memory loss; confusion; depression; tiredness; upset stomach.

Tell your doctor if you have any side effect that bothers you or that does not go away.

These are not all the possible side effects of LYPQOZET . For more information, ask your doctor or pharmacist.

Call your doctor for medical advice about side effects. You may report side effects to FDA at 1-800-FDA-1088.

How should I store LYPQOZET?

- Store LYPQOZET at room temperature between 68° to 77°F (20° to 25°C).
- Keep LYPQOZET dry and out of the light.

Keep LYPQOZET and all medicines out of the reach of children.

General information about the safe and effective use of LYPQOZET.
LYPQOZET may help to reduce your cholesterol in 2 ways. It reduces the cholesterol absorbed in your digestive tract, as well as the cholesterol your body makes by itself. LYPQOZET do not help you lose weight.

Medicines are sometimes prescribed for purposes other than those listed in the Patient Information leaflet. Do not use LYPQOZET for a condition for which it was not prescribed. Do not give LYPQOZET to other people, even if they have the same problem that you have. It may harm them.

This Patient Information leaflet summarizes the most important information about LYPQOZET. If you would like more information, talk with your doctor. You can ask your pharmacist or doctor for information about LYPQOZET that is written for health professionals.

For more information, call Althera at 1-877-495-3908.

What are the ingredients in LYPQOZET?
Active ingredients: ezetimibe and atorvastatin
Inactive ingredients: calcium carbonate, colloidal silicon dioxide, croscarmellose sodium, hydroxypropyl cellulose, hypromellose, lactose monohydrate, magnesium stearate, microcrystalline cellulose, polyethylene glycol 8000, polysorbate 80, red 30 iron oxide, sodium lauryl sulfate, talc and titanium dioxide.

This Patient Information has been approved by the U.S. Food and Drug Administration

Manufacturer for:
Althera Pharmaceuticals, LLC.,
1201 N Orange St, Suite 712,
Wilmington, DE 19801

Distributed by:
Althera Pharmaceuticals, LLC.,
Wilmington, DE 19801 USA

Revised: January 2024

Reference ID: AL-310-000-3

PACKAGE/LABEL DISPLAY PANEL – 10 mg/10 mg

NDC 70661-005-30

LYPQOZET

(ezetimibe and atorvastatin) tablets

10 mg/10 mg

30 Tablets

Rx Only

Each Film-Coated Tablet Contains:

10 mg of ezetimibe, USP and 10.34 mg of atorvastatin calcium, USP, equivalent to 10 mg of atorvastatin.

Dispense in a tight, light resistant container as defined in the USP.

Keep out of reach of children.

Usual Adult Dosage: See package outsert for full Prescribing Information.

Store at 20°C to 25°C (68°F to 77°F); excursions permitted to 15°C to 30°C (59°F to 86°F) [See USP Controlled Room Temperature].

Protect from moisture and light.

Distributed by:

Althera Pharmaceuticals, LLC,

Wilmington, DE 19801 USA

Manufactured for:

Althera Pharmaceuticals, LLC,

Wilmington, DE 19801

MADE IN INDIA

CODE: MP/DRUGS/25/10/92

Rev. 01/2024 EM 15757 XXXXXXX

NDC 70661-005-90

LYPQOZET

(ezetimibe and atorvastatin) tablets

10 mg/10 mg

90 Tablets

Rx Only

Each Film-Coated Tablet Contains:

10 mg of ezetimibe, USP and 10.34 mg of atorvastatin calcium, USP, equivalent to 10 mg of atorvastatin.

Dispense in a tight, light resistant container as defined in the USP.

Keep out of reach of children.

Usual Adult Dosage: See package outsert for full Prescribing Information.

Store at 20°C to 25°C (68°F to 77°F); excursions permitted to 15°C to 30°C (59°F to 86°F) [See USP Controlled Room Temperature].

Protect from moisture and light.

Distributed by:

Althera Pharmaceuticals, LLC,

Wilmington, DE 19801 USA

Manufactured for:

Althera Pharmaceuticals, LLC,

Wilmington, DE 19801

MADE IN INDIA

CODE: MP/DRUGS/25/10/92

Rev. 01/2024 EM 15759 XXXXXXX

PACKAGE/LABEL DISPLAY PANEL – 10 mg/20 mg

NDC 70661-006-30

LYPQOZET

(ezetimibe and atorvastatin) tablets

10 mg/20 mg

30 Tablets

Rx Only

Each Film-Coated Tablet Contains:

10 mg of ezetimibe, USP and 20.68 mg of atorvastatin calcium, USP, equivalent to 20 mg of atorvastatin.

Dispense in a tight, light resistant container as defined in the USP.

Keep out of reach of children.

Usual Adult Dosage: See package outsert for full Prescribing Information.

Store at 20°C to 25°C (68°F to 77°F); excursions permitted to 15°C to 30°C (59°F to 86°F) [See USP Controlled Room Temperature].

Protect from moisture and light.

Distributed by:

Althera Pharmaceuticals LLC,

Wilmington, DE 19801 USA

Manufactured for:

Althera Pharmaceuticals, LLC,

Wilmington, DE 19801

MADE IN INDIA

CODE: MP/DRUGS/25/10/92

Rev. 01/2024 EM 15760 XXXXXXX

NDC 70661-006-90

LYPQOZET

(ezetimibe and atorvastatin) tablets

10 mg/20 mg

90 Tablets

Rx Only

Each Film-Coated Tablet Contains:

10 mg of ezetimibe, USP and 20.68 mg of atorvastatin calcium, USP, equivalent to 20 mg of atorvastatin.

Dispense in a tight, light resistant container as defined in the USP.

Keep out of reach of children.

Usual Adult Dosage: See package outsert for full Prescribing Information.

Store at 20°C to 25°C (68°F to 77°F); excursions permitted to 15°C to 30°C (59°F to 86°F) [See USP Controlled Room Temperature].

Protect from moisture and light.

Distributed by:

Althera Pharmaceuticals, LLC,

Wilmington, DE 19801 USA

Manufactured for:

Althera Pharmaceuticals, LLC,

Wilmington, DE 19801

MADE IN INDIA

CODE: MP/DRUGS/25/10/92

Rev. 01/2024 EM 15760 XXXXXXX

PACKAGE/LABEL DISPLAY PANEL – 10 mg/40 mg

NDC 70661-007-30

LYPQOZET

(ezetimibe and atorvastatin) tablets

10 mg/40 mg

30 Tablets

Rx Only

Each Film-Coated Tablet Contains:

10 mg of ezetimibe, USP and 41.37 mg of atorvastatin calcium, USP, equivalent to 40 mg of atorvastatin.

Dispense in a tight, light resistant container as defined in the USP.
Keep out of reach of children.

Usual Adult Dosage: See package outsert for full Prescribing Information.

Store at 20°C to 25°C (68°F to 77°F); excursions permitted to 15°C to 30°C (59°F to 86°F) [See USP Controlled Room Temperature].

Protect from moisture and light.

Distributed by:

Althera Pharmaceuticals, LLC,

Wilmington, DE, 19801, USA

Manufactured for:

Althera Pharmaceuticals, LLC,

Wilmington, DE 19801

MADE IN INDIA

CODE: MP/DRUGS/25/10/92

Rev. 01/2024 EM 15761 XXXXXXX

NDC 70661-007-90

LYPQOZET

(ezetimibe and atorvastatin) tablets

10 mg/40 mg

90 Tablets

Rx Only

Each Film-Coated Tablet Contains:

10 mg of ezetimibe, USP and 41.37 mg of atorvastatin calcium, USP, equivalent to 40 mg of atorvastatin.

Dispense in a tight, light resistant container as defined in the USP.
Keep out of reach of children.

Usual Adult Dosage: See package outsert for full Prescribing Information.

Store at 20°C to 25°C (68°F to 77°F); excursions permitted to 15°C to 30°C (59°F to 86°F) [See USP Controlled Room Temperature].
Protect from moisture and light.

Distributed by:

Althera Pharmaceuticals LLC,

Wilmington, DE 19801 USA

Manufactured for:

Althera Pharmaceuticals, LLC,

Wilmington, DE 19801

MADE IN INDIA

CODE: MP/DRUGS/25/10/92

Rev. 01/2024 EM 15762 XXXXXXX

PACKAGE/LABEL DISPLAY PANEL – 10 mg/80 mg

NDC 70661-008-30

LYPQOZET

(ezetimibe and atorvastatin) tablets

10 mg/80 mg

30 Tablets

Rx Only

Each Film-Coated Tablet Contains:

10 mg of ezetimibe, USP and 82.73 mg of atorvastatin calcium, USP, equivalent to 80 mg of atorvastatin.

Dispense in a tight, light resistant container as defined in the USP.
Keep out of reach of children.

Usual Adult Dosage: See package outsert for full Prescribing Information.

Store at 20°C to 25°C (68°F to 77°F); excursions permitted to 15°C to 30°C (59°F to 86°F) [See USP Controlled Room Temperature].
Protect from moisture and light.

Distributed by:

Althera Pharmaceuticals, LLC,

Wilmington, DE 19801 USA

Manufactured for:

Althera Pharmaceuticals, LLC,

Wilmington, DE 19801

MADE IN INDIA

CODE: MP/DRUGS/25/10/92

Rev. 01/2024 EM 15763 XXXXXXX

NDC 70661-008-90

LYPQOZET

(ezetimibe and atorvastatin) tablets

10 mg/80 mg

90 Tablets

Rx Only

Each Film-Coated Tablet Contains:

10 mg of ezetimibe, USP and 82.73 mg of atorvastatin calcium, USP, equivalent to 80 mg of atorvastatin.

Dispense in a tight, light resistant container as defined in the USP.
Keep out of reach of children.

Usual Adult Dosage: See package outsert for full Prescribing Information.
Store at 20°C to 25°C (68°F to 77°F); excursions permitted to 15°C to 30°C (59°F to 86°F) [See USP Controlled Room Temperature].
Protect from moisture and light.

Distributed by:

Althera Pharmaceuticals, LLC,

Wilmington, DE 19801 USA

Manufactured for:

Althera Pharmaceuticals, LLC,

Wilmington, DE 19801

MADE IN INDIA

CODE: MP/DRUGS/25/10/92

Rev. 01/2024 EM 15764 XXXXXXX